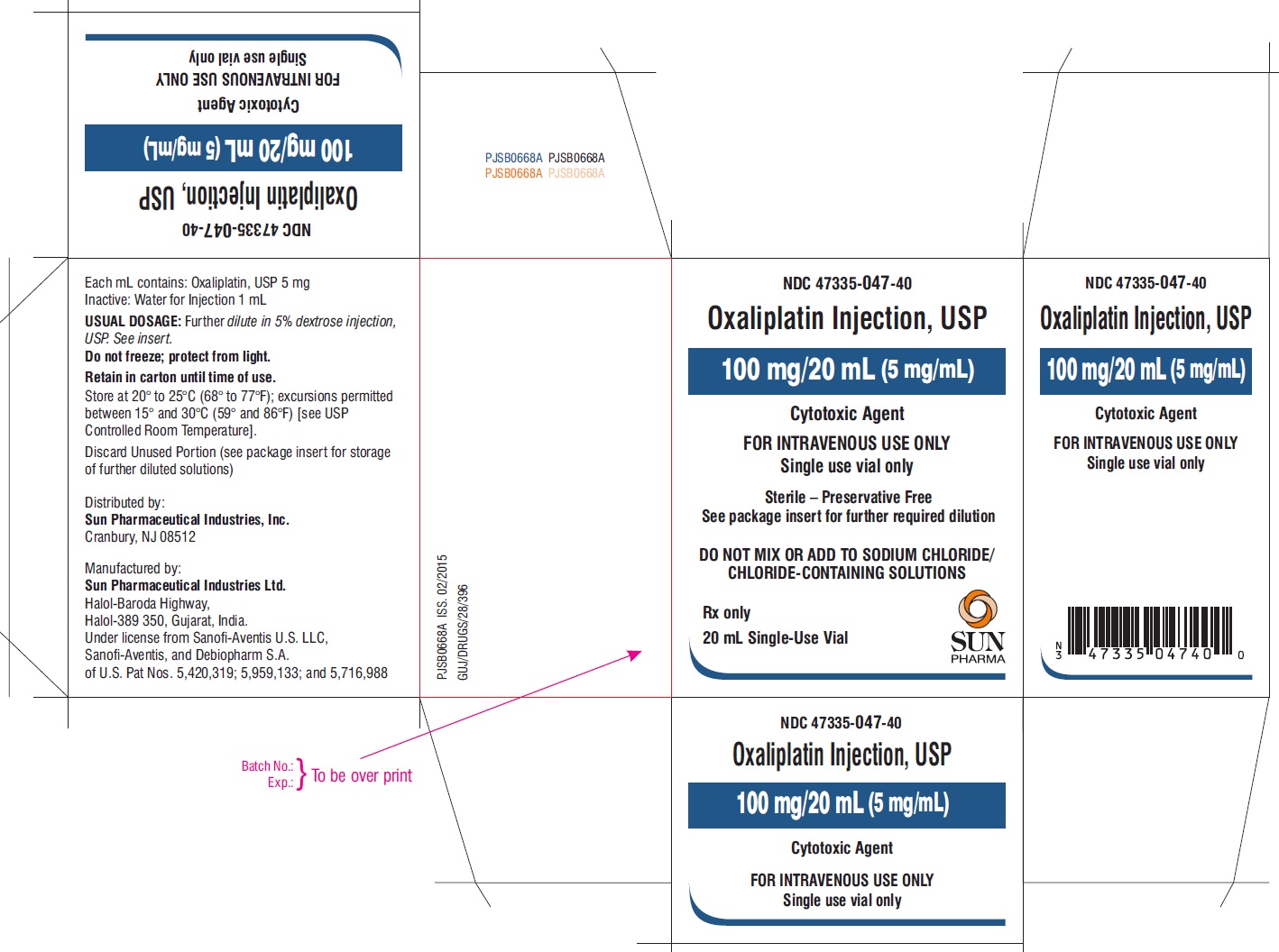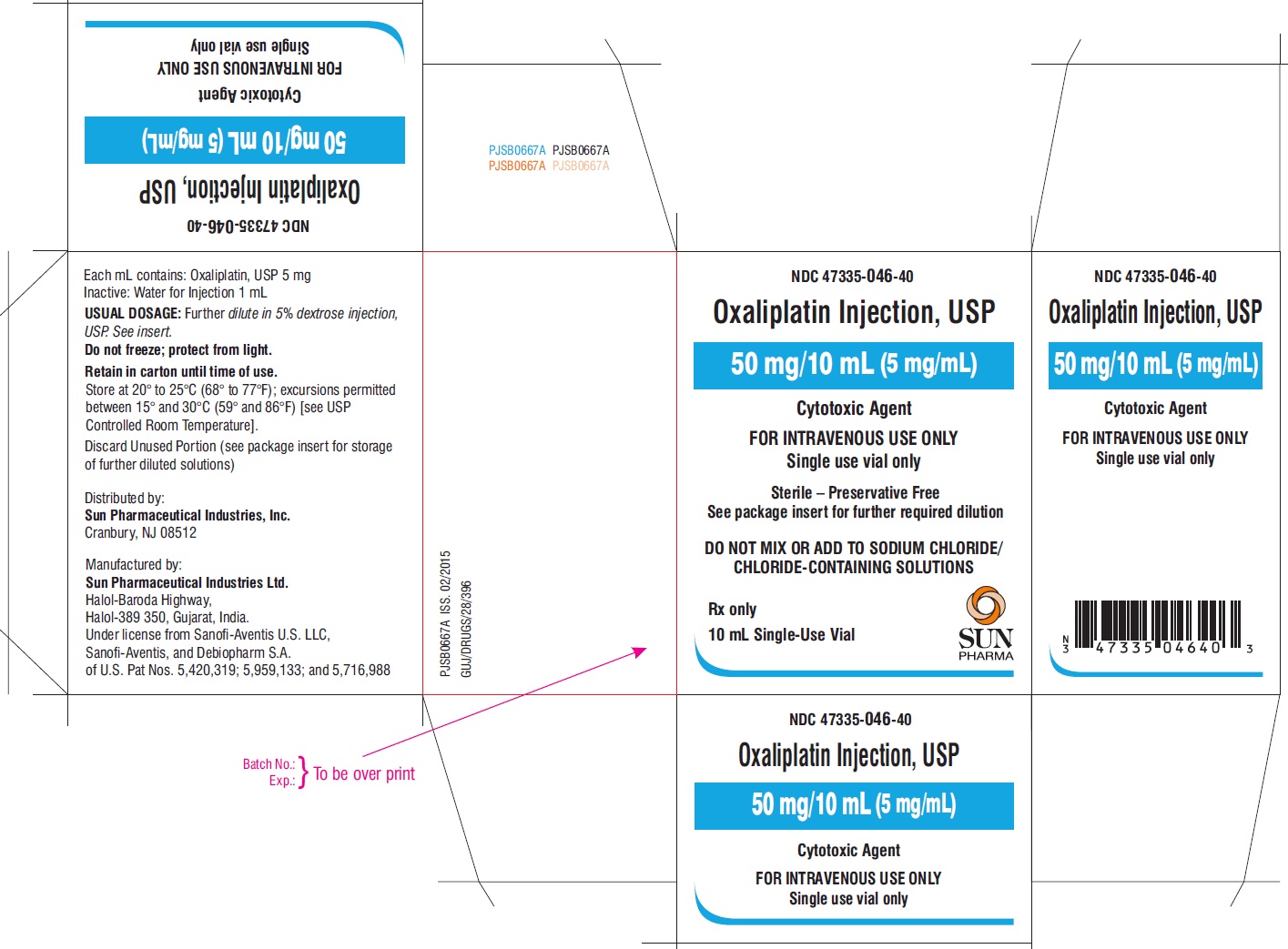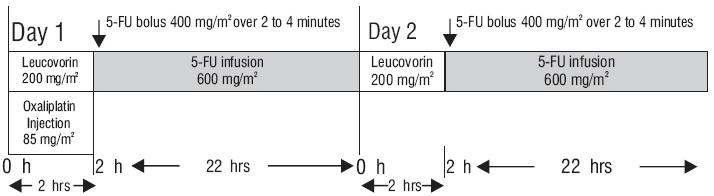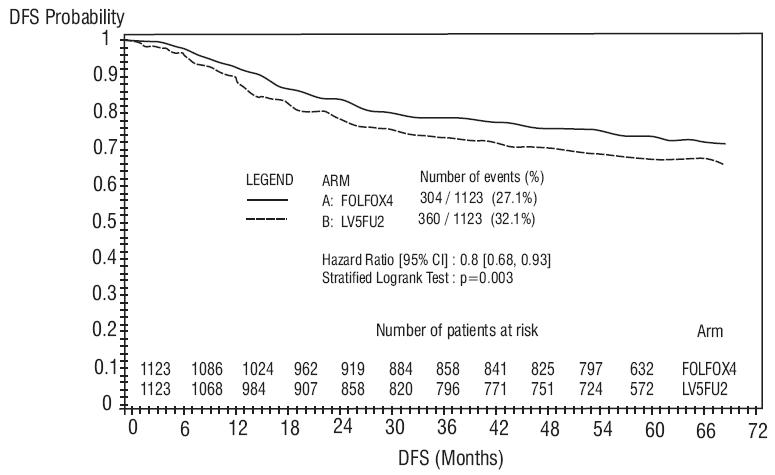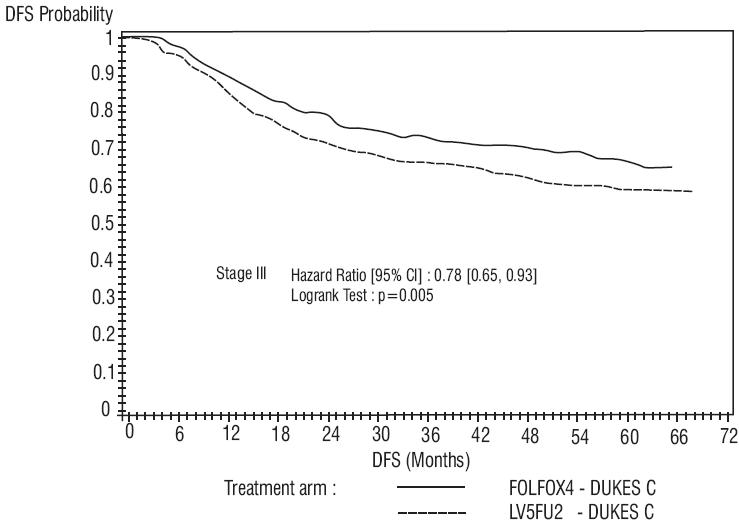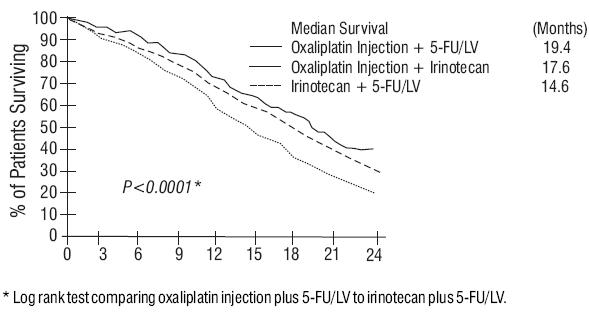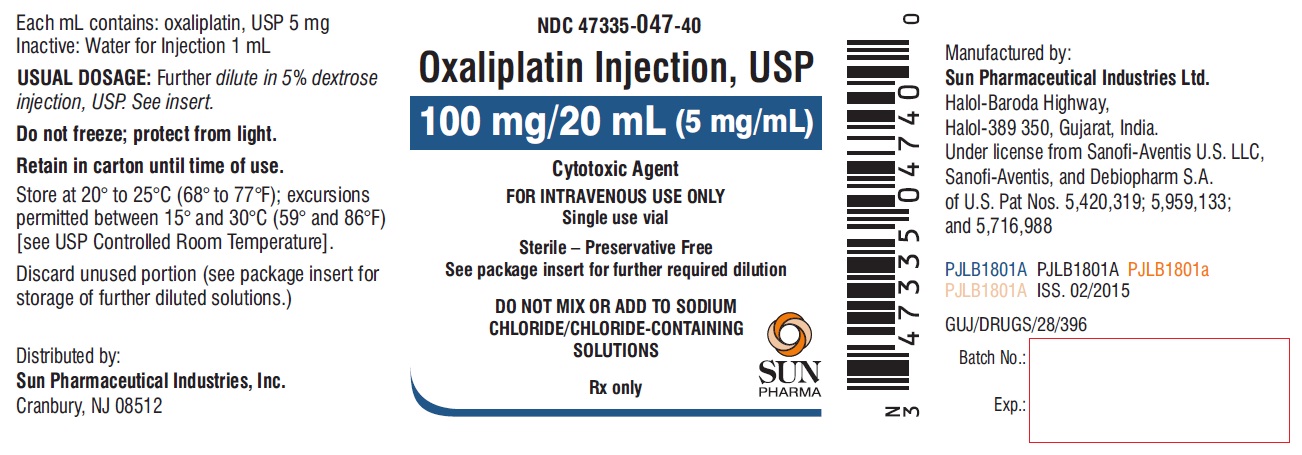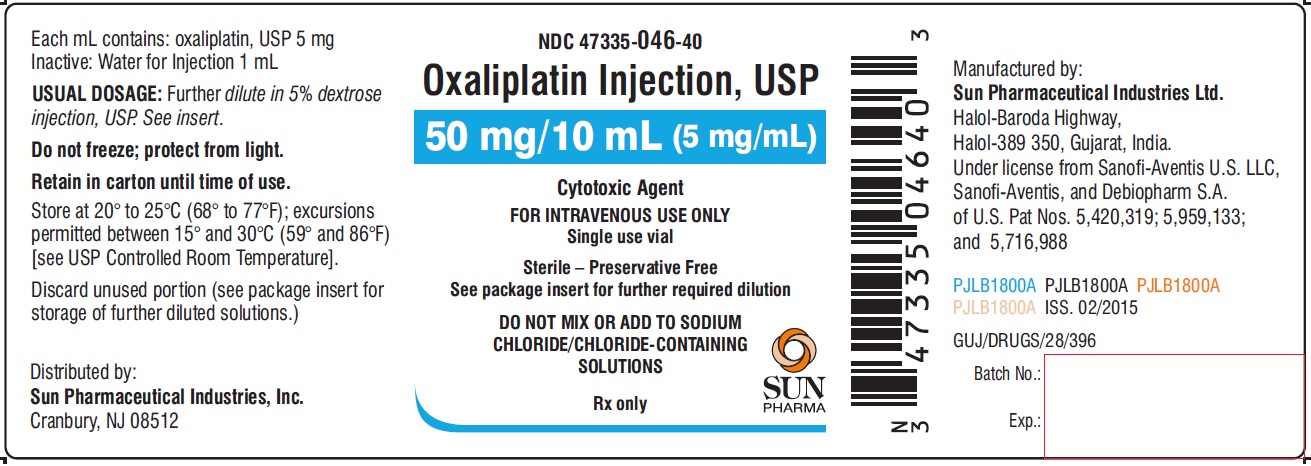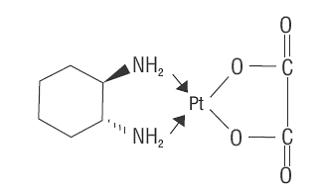 DRUG LABEL: Oxaliplatin
NDC: 47335-046 | Form: INJECTION, SOLUTION, CONCENTRATE
Manufacturer: Sun Pharmaceutical Industries, Inc.
Category: prescription | Type: Human Prescription Drug Label
Date: 20181031

ACTIVE INGREDIENTS: OXALIPLATIN 50 mg/10 mL
INACTIVE INGREDIENTS: WATER

HIGHLIGHTS OF PRESCRIBING INFORMATION

These highlights do not include all the information needed to use OXALIPLATIN INJECTION safely and effectively. See full prescribing information for OXALIPLATIN INJECTION.
OXALIPLATIN injection,
for intravenous use
Initial U.S. Approval: 2002

RECENT MAJOR CHANGES

Dosage and Administration (2.2) 10/2015

Warnings and Precautions (5.3, 5.4,5.7, 5.8, 5.9) 10/2015

WARNING: ANAPHYLACTIC REACTIONS

See full prescribing information for complete boxed warning.
Anaphylactic reactions to oxaliplatin injection have been reported, and may occur within minutes of oxaliplatin injection administration. Epinephrine, corticosteroids, and antihistamines have been employed to alleviate symptoms. (5.1)

1 INDICATIONS AND USAGE

Oxaliplatin injection is a platinum-based drug used in combination with infusional 5-fluorouracil/leucovorin, which is indicated for:

- adjuvant treatment of stage III colon cancer in patients who have undergone complete resection of the primary tumor. (1)
- treatment of advanced colorectal cancer. (1)

2 DOSAGE AND ADMINISTRATION

- Administer oxaliplatin injection in combination with 5-fluorouracil/leucovorin every 2 weeks. (2.1):
  - Day 1: Oxaliplatin injection 85 mg/m^2 intravenous infusion in 250 to 500 mL 5% Dextrose Injection, USP and leucovorin 200 mg/m^2 intravenous infusion in 5% Dextrose Injection, USP both given over 120 minutes at the same time in separate bags using a Y-line, followed by 5-fluorouracil 400 mg/m^2 intravenous bolus given over 2 to 4 minutes, followed by 5-fluorouracil 600 mg/m^2 intravenous infusion in 500 mL 5% Dextrose Injection, USP (recommended) as a 22-hour continuous infusion.
  - Day 2: leucovorin 200 mg/m^2 intravenous infusion over 120 minutes, followed by 5-fluorouracil 400 mg/m^2 intravenous bolus given over 2 to 4 minutes, followed by 5-fluorouracil 600 mg/m^2 intravenous infusion in 500 mL 5% Dextrose Injection, USP (recommended) as a 22-hour continuous infusion.
- Reduce the dose of oxaliplatin injection to 75 mg/m^2 (adjuvant setting) or 65 mg/m^2 (advanced colorectal cancer) (2.2):
  - if there are persistent grade 2 neurosensory events that do not resolve.
  - after recovery from grade 3/4 gastrointestinal toxicities (despite prophylactic treatment) or grade 4 neutropenia or febrile neutropenia or grade 3/4 thrombocytopenia. Delay next dose until neutrophils ≥1.5 x 10^9/L and platelets ≥75 x 10^9/L.
- For patients with severe renal impairment (creatinine clearance <30 mL/min), the initial recommended dose is 65 mg/m². (2.2)
- Discontinue oxaliplatin injection if there are persistent Grade 3 neurosensory events. (2.2)
- Never prepare a final dilution with a sodium chloride solution or other chloride-containing solutions. (2.3)

3 DOSAGE FORMS AND STRENGTHS

Single-use vials of 50 mg or 100 mg oxaliplatin as a sterile, preservative-free, aqueous solution at a concentration of 5 mg/mL. (3)

4 CONTRAINDICATIONS

- Known allergy to oxaliplatin injection or other platinum compounds. (4, 5.1)

5 WARNINGS AND PRECAUTIONS

- Allergic Reactions: Monitor for development of rash, urticaria, erythema, pruritis, bronchospasm, and hypotension. (5.1)
- Neuropathy: Reduce the dose or discontinue oxaliplatin injection if necessary. (5.2)
- Severe Neutropenia: Delay oxaliplatin injection until neutrophils are ≥1.5 x 109/L.Withhold oxaliplatin injection for sepsis. (5.3)
- Pulmonary Toxicity: May need to discontinue oxaliplatin injection until interstitial lung disease or pulmonary fibrosis are excluded. (5.4)
- Hepatotoxicity: Monitor liver function tests. (5.5)
- Cardiovascular Toxicity: Correct hypokalemia or hypomagnesemia prior to initiating oxaliplatin injection. (5.6)
- Rhabdomyolysis: Discontinue oxaliplatin injection if rhabdomyolysis occurs. (5.7)
- Pregnancy. Fetal harm can occur when administered to a pregnant woman. Women should be apprised of the potential harm to the fetus. (5.8, 8.1)

6 ADVERSE REACTIONS

Most common adverse reactions (incidence ≥ 40%) were peripheral sensory neuropathy, neutropenia, thrombocytopenia, anemia, nausea, increase in transaminases and alkaline phosphatase, diarrhea, emesis, fatigue and stomatitis. Other adverse reactions, including serious adverse reactions, have been reported. (6.1)
To report SUSPECTED ADVERSE REACTIONS, contact Sun Pharmaceutical Industries, Inc. 1-800-818-4555 or FDA at 1-800-FDA-1088 or www.fda.gov/medwatch.

FULL PRESCRIBING INFORMATION

WARNING: ANAPHYLACTIC REACTIONS

Anaphylactic reactions to oxaliplatin injection have been reported, and may occur within minutes of oxaliplatin injection administration. Epinephrine, corticosteroids, and antihistamines have been employed to alleviate symptoms of anaphylaxis [see Warnings and Precautions (5.1)].

1 INDICATIONS AND USAGE

Oxaliplatin injection, USP, used in combination with infusional 5-fluorouracil/leucovorin, is indicated for:

- adjuvant treatment of stage III colon cancer in patients who have undergone complete resection of the primary tumor.
- treatment of advanced colorectal cancer.

2 DOSAGE AND ADMINISTRATION

Oxaliplatin injection should be administered under the supervision of a qualified physician experienced in the use of cancer chemotherapeutic agents. Appropriate management of therapy and complications is possible only when adequate diagnostic and treatment facilities are readily available.

2.1 Dosage

Administer oxaliplatin injection in combination with 5-fluorouracil/leucovorin every 2 weeks. For advanced disease, treatment is recommended until disease progression or unacceptable toxicity. For adjuvant use, treatment is recommended for a total of 6 months (12 cycles):
Day 1: Oxaliplatin injection 85 mg/m^2 intravenous infusion in 250 to 500 mL 5% Dextrose injection, USP and leucovorin 200 mg/m^2 intravenous infusion in 5% Dextrose Injection, USP both given over 120 minutes at the same time in separate bags using a Y-line, followed by 5-fluorouracil 400 mg/m^2 intravenous bolus given over 2 to 4 minutes, followed by 5-fluorouracil 600 mg/m^2 intravenous infusion in 500 mL 5% Dextrose Injection, USP (recommended) as a 22-hour continuous infusion.
Day 2: Leucovorin 200 mg/m^2 intravenous infusion over 120 minutes, followed by 5-fluorouracil 400 mg/m^2 intravenous bolus given over 2 to 4 minutes, followed by 5-fluorouracil 600 mg/m^2 intravenous infusion in 500 mL 5% Dextrose Injection, USP (recommended) as a 22-hour continuous infusion.
Figure 1

The administration of oxaliplatin injection does not require prehydration. Premedication with antiemetics, including 5-HT3 blockers with or without dexamethasone, is recommended.
For information on 5-fluorouracil and leucovorin, see the respective package inserts.

2.2 Dose Modification Recommendations

Prior to subsequent therapy cycles, patients should be evaluated for clinical toxicities and recommended laboratory tests [see Warnings and Precautions (5.11)]. Prolongation of infusion time for oxaliplatin injection from 2 hours to 6 hours may mitigate acute toxicities. The infusion times for 5-fluorouracil and leucovorin do not need to be changed.
Adjuvant Therapy in Patients with Stage III Colon Cancer
Neuropathy and other toxicities were graded using the NCI CTC scale version 1 [see Warnings and Precautions (5.2)].
For patients who experience persistent Grade 2 neurosensory events that do not resolve, a dose reduction of oxaliplatin injection to 75 mg/m^2 should be considered. For patients with persistent Grade 3 neurosensory events, discontinuing therapy should be considered. The infusional 5-fluorouracil/leucovorin regimen need not be altered.
A dose reduction of oxaliplatin injection to 75 mg/m^2 and infusional 5-fluorouracil to 300 mg/m^2 bolus and 500 mg/m^2 22 hour infusion is recommended for patients after recovery from grade 3/4 gastrointestinal (despite prophylactic treatment)or grade 4 neutropenia, or febrile neutropenia, or grade 3/4 thrombocytopenia. The next dose should be delayed until: neutrophils ≥1.5 x 10^9/L and platelets ≥75 x 10^9/L.
Dose Modifications in Therapy in Previously Untreated and Previously Treated Patients with Advanced Colorectal Cancer
Neuropathy was graded using a study-specific neurotoxicity scale [see Warnings and Precautions (5.2)]. Other toxicities were graded by the NCI CTC, Version 2.
For patients who experience persistent Grade 2 neurosensory events that do not resolve, a dose reduction of oxaliplatin injection to 65 mg/m^2 should be considered. For patients with persistent Grade 3 neurosensory events, discontinuing therapy should be considered. The 5-fluorouracil/leucovorin regimen need not be altered.
A dose reduction of oxaliplatin injection to 65 mg/m^2 and 5-fluorouracil by 20% (300 mg/m^2 bolus and 500 mg/m^2 22-hour infusion) is recommended for patients after recovery from grade 3/4 gastrointestinal (despite prophylactic treatment) or grade 4 neutropenia, or febrile neutropenia, or grade 3/4 thrombocytopenia. The next dose should be delayed until: neutrophils ≥1.5 x 10^9/L and platelets ≥75 x 10^9/L.
Dose Modifications in Therapy for Patients with Renal Impairment
In patients with normal renal function or mild to moderate renal impairment, the recommended dose of oxaliplatin injection is 85 mg/m^2. In patients with severe renal impairment, the initial recommended oxaliplatin injection dose should be reduced to 65 mg/m^2 [see Use in Specific Populations (8.6) and Clinical Pharmacology (12.3)].

2.3 Preparation of Infusion Solution

Do not freeze and protect from light the concentrated solution.
A final dilution must never be performed with a sodium chloride solution or other chloride-containing solutions.
The solution must be further diluted in an infusion solution of 250 to 500 mL of 5% Dextrose Injection, USP. After dilution with 250 to 500 mL of 5% Dextrose Injection, USP, the shelf life is 6 hours at room temperature [20° to 25°C (68° to 77°F)] or up to 24 hours under refrigeration [2° to 8°C (36° to 46°F)].
After final dilution, protection from light is not required.
Oxaliplatin injection is incompatible in solution with alkaline medications or media (such as basic solutions of 5-fluorouracil) and must not be mixed with these or administered simultaneously through the same infusion line. The infusion line should be flushed with 5% Dextrose Injection, USP prior to administration of any concomitant medication.
Parenteral drug products should be inspected visually for particulate matter and discoloration prior to administration and discarded if present.
Needles or intravenous administration sets containing aluminum parts that may come in contact with oxaliplatin injection should not be used for the preparation or mixing of the drug. Aluminum has been reported to cause degradation of platinum compounds.

3 DOSAGE FORMS AND STRENGTHS

Oxaliplatin injection is supplied in single-use vials containing 50 mg or 100 mg of oxaliplatin, USP as a sterile, preservative-free, aqueous solution at a concentration of 5 mg/mL.

4 CONTRAINDICATIONS

Oxaliplatin injection should not be administered to patients with a history of known allergy to oxaliplatin injection or other platinum compounds [see Warnings and Precautions (5.1)].

5 WARNINGS AND PRECAUTIONS

5.1 Allergic Reactions

See boxed warning
Grade 3/4 hypersensitivity, including anaphylactic/anaphylactoid reactions, to oxaliplatin injection has been observed in 2 to 3% of colon cancer patients. These allergic reactions which can be fatal, can occur within minutes of administration and at any cycle, and were similar in nature and severity to those reported with other platinum-containing compounds, such as rash, urticaria, erythema, pruritus, and, rarely, bronchospasm and hypotension. The symptoms associated with hypersensitivity reactions reported in the previously untreated patients were urticaria, pruritus, flushing of the face, diarrhea associated with oxaliplatin infusion, shortness of breath, bronchospasm, diaphoresis, chest pains, hypotension, disorientation and syncope. These reactions are usually managed with standard epinephrine, corticosteroid, antihistamine therapy, and require discontinuation of therapy. Rechallenge is contraindicated in these patients [see Contraindications (4)]. Drug-related deaths associated with platinum compounds from anaphylaxis have been reported.

5.2 Neurologic Toxicity

Neuropathy
Oxaliplatin injection is associated with two types of neuropathy:
An acute, reversible, primarily peripheral, sensory neuropathy that is of early onset, occurring within hours or one to two days of dosing, that resolves within 14 days, and that frequently recurs with further dosing. The symptoms may be precipitated or exacerbated by exposure to cold temperature or cold objects and they usually present as transient paresthesia, dysesthesia and hypoesthesia in the hands, feet, perioral area, or throat. Jaw spasm, abnormal tongue sensation, dysarthria, eye pain, and a feeling of chest pressure have also been observed. The acute, reversible pattern of sensory neuropathy was observed in about 56% of study patients who received oxaliplatin injection with 5-fluorouracil/leucovorin. In any individual cycle acute neurotoxicity was observed in approximately 30% of patients. In adjuvant patients the median cycle of onset for grade 3 peripheral sensory neuropathy was 9 in the previously treated patients the median number of cycles administered on the oxaliplatin injection with 5-fluorouracil/leucovorin combination arm was 6.
An acute syndrome of pharyngolaryngeal dysesthesia seen in 1 to 2% (grade 3/4) of patients previously untreated for advanced colorectal cancer, and the previously treated patients, is characterized by subjective sensations of dysphagia or dyspnea, without any laryngospasm or bronchospasm (no stridor or wheezing). Ice (mucositis prophylaxis) should be avoided during the infusion of oxaliplatin injection because cold temperature can exacerbate acute neurological symptoms.
A persistent (>14 days), primarily peripheral, sensory neuropathy that is usually characterized by paresthesias, dysesthesias, hypoesthesias, but may also include deficits in proprioception that can interfere with daily activities (e.g., writing, buttoning, swallowing, and difficulty walking from impaired proprioception). These forms of neuropathy occurred in 48% of the study patients receiving oxaliplatin injection with 5-fluorouracil/leucovorin. Persistent neuropathy can occur without any prior acute neuropathy event. The majority of the patients (80%) who developed grade 3 persistent neuropathy progressed from prior Grade 1 or 2 events. These symptoms may improve in some patients upon discontinuation of oxaliplatin injection.
In the adjuvant colon cancer trial, neuropathy was graded using a prelisted module derived from the Neuro-Sensory section of the National Cancer Institute Common Toxicity Criteria (NCI CTC) scale, Version 1, as follows:

Table 1 - NCI CTC Grading for Neuropathy in Adjuvant Patients
Grade | Definition
Grade 0 | No change or none
Grade 1 | Mild paresthesias, loss of deep tendon reflexes
Grade 2 | Mild or moderate objective sensory loss, moderate paresthesias
Grade 3 | Severe objective sensory loss or paresthesias that interfere with function
Grade 4 | Not applicable

Peripheral sensory neuropathy was reported in adjuvant patients treated with the oxaliplatin injection combination with a frequency of 92% (all grades) and 13% (grade 3). At the 28-day follow-up after the last treatment cycle, 60% of all patients had any grade (Grade 1=40%, Grade 2=16%, Grade 3=5%) peripheral sensory neuropathy decreasing to 39% at 6 months follow-up (Grade 1=31%, Grade 2=7%, Grade 3=1%) and 21% at 18 months of follow-up (Grade 1=17%, Grade 2=3%, Grade 3=1%).
In the advanced colorectal cancer studies, neuropathy was graded using a study-specific neurotoxicity scale, which was different from the NCI CTC scale, Version 2 (see below).

Table 2 - Grading Scale for Paresthesias/Dysesthesias in Advanced Colorectal Cancer Patients
Grade | Definition
Grade 1 | Resolved and did not interfere with functioning
Grade 2 | Interfered with function but not daily activities
Grade 3 | Pain or functional impairment that interfered with daily activities
Grade 4 | Persistent impairment that is disabling or life-threatening

Overall, neuropathy was reported in patients previously untreated for advanced colorectal cancer in 82% (all grades) and 19% (grade 3/4), and in the previously treated patients in 74% (all grades) and 7% (grade 3/4) events. Information regarding reversibility of neuropathy was not available from the trial for patients who had not been previously treated for colorectal cancer.
Reversible Posterior Leukoencephalopathy Syndrome
Reversible Posterior Leukoencephalopathy Syndrome (RPLS, also known as PRES, Posterior Reversible Encephalopathy Syndrome) has been observed in clinical trials (< 0.1%) and postmarketing experience. Signs and symptoms of RPLS could be headache, altered mental functioning, seizures, abnormal vision from blurriness to blindness, associated or not with hypertension [see Adverse Reactions (6.2)]. Diagnosis of RPLS is based upon confirmation by brain imaging.

5.3 Severe Neutropenia

Grade 3 or 4 neutropenia occurred in 41-44% of patients with colorectal cancer treated with oxaliplatin injection in combination with 5-fluorouracil (5-FU) and leucovorin compared to 5% with 5-FU plus leucovorin alone. Sepsis, neutropenic sepsis and septic shock have been reported in patients treated with oxaliplatin injection, including fatal outcomes [see Adverse Reactions (6.1)].

Delay oxaliplatin injection until neutrophils are ≥ 1.5 x 109/L. Withhold oxaliplatin injection for sepsis or septic shock. Dose reduce oxaliplatin injection after recovery from Grade 4 neutropenia or febrile neutropenia [see Dosage and Administration (2.2)].

5.4 Pulmonary Toxicity

Oxaliplatin injection has been associated with pulmonary fibrosis (<1% of study patients), which may be fatal. The combined incidence of cough and dyspnea was 7.4% (any grade) and <1% (grade 3) with no grade 4 events in the oxaliplatin injection plus infusional 5-fluorouracil/leucovorin arm compared to 4.5% (any grade) and no grade 3 and 0.1% grade 4 events in the infusional 5-fluorouracil/leucovorin alone arm in adjuvant colon cancer patients. In this study, one patient died from eosinophilic pneumonia in the oxaliplatin injection combination arm. The combined incidence of cough, dyspnea and hypoxia was 43% (any grade) and 7% (grade 3 and 4) in the oxaliplatin injection plus 5-fluorouracil/leucovorin arm compared to 32% (any grade) and 5% (grade 3 and 4) in the irinotecan plus 5-fluorouracil/leucovorin arm of unknown duration for patients with previously untreated colorectal cancer. In case of unexplained respiratory symptoms such as non-productive cough, dyspnea, crackles, or radiological pulmonary infiltrates, oxaliplatin injection should be discontinued until further pulmonary investigation excludes interstitial lung disease or pulmonary fibrosis.

5.5 Hepatotoxicity

Hepatotoxicity as evidenced in the adjuvant study, by increase in transaminases (57% vs. 34%) and alkaline phosphatase (42% vs. 20%) was observed more commonly in the oxaliplatin injection combination arm than in the control arm. The incidence of increased bilirubin was similar on both arms. Changes noted on liver biopsies include: peliosis, nodular regenerative hyperplasia or sinusoidal alterations, perisinusoidal fibrosis, and veno-occlusive lesions. Hepatic vascular disorders should be considered, and if appropriate, should be investigated in case of abnormal liver function test results or portal hypertension, which cannot be explained by liver metastases [see Clinical Trials Experience (6.1)].

5.6 Cardiovascular Toxicity

QT prolongation and ventricular arrhythmias including fatal Torsade de Pointes have been reported in postmarketing experiences following oxaliplatin injection administration. ECG monitoring is recommended if therapy is initiated in patients with congestive heart failure, bradyarrhythmias, drugs known to prolong the QT interval, including Class Ia and III antiarrhythmics, and electrolyte abnormalities. Correct hypokalemia or hypomagnesemia prior to initiating oxaliplatin injection and monitor these electrolytes periodically during therapy. Avoid oxaliplatin injection in patients with congenital long QT syndrome [see Adverse Reactions (6.2)].

5.7 Rhabdomyolysis

Rhabdomyolysis, including fatal cases, has been reported in patients treated with oxaliplatin injection. Discontinue oxaliplatin injection if any signs or symptoms of rhabdomyolysis occur. [see Adverse Reactions (6.2)].

5.8 Use in Pregnancy

Pregnancy Category D
Oxaliplatin injection may cause fetal harm when administered to a pregnant woman. There are no adequate and well-controlled studies of oxaliplatin injection in pregnant women. Women of childbearing potential should be advised to avoid becoming pregnant while receiving treatment with oxaliplatin injection. [see Use in Specific Populations (8.1)].

5.9 Recommended Laboratory Tests

Standard monitoring of the white blood cell count with differential, hemoglobin, platelet count, and blood chemistries (including ALT, AST, bilirubin and creatinine) is recommended before each oxaliplatin injection cycle [see Dosage and Administration (2)].
There have been reports while on study and from postmarketing surveillance of prolonged prothrombin time and INR occasionally associated with hemorrhage in patients who received oxaliplatin injection plus 5-fluorouracil/leucovorin while on anticoagulants. Patients receiving oxaliplatin injection plus 5-fluorouracil/leucovorin and requiring oral anticoagulants may require closer monitoring.

6 ADVERSE REACTIONS

The following serious adverse reactions are discussed in greater detail in other sections of the label:
• Anaphylaxis and Allergic reactions [see Boxed Warning, Warnings and Precautions (5.1).]
• Neuropathy [see Warnings and Precautions (5.2).]
• Severe Neutropenia [see Warnings and Precautions (5.3).]
• Pulmonary Toxicities [see Warnings and Precautions (5.4).]
• Hepatotoxicity [see Warnings and Precautions (5.5).]
• Cardiovascular Toxicities [see Warnings and Precautions (5.6).]
• Rhabdomyolysis [see Warnings and Precautions (5.7).]

6.1 Clinical Trials Experience

Because clinical trials are conducted under widely varying conditions, adverse reaction rates observed in the clinical trials of a drug cannot be directly compared to rates in the clinical trials of another drug and may not reflect the rates observed in practice.
More than 1100 patients with stage II or III colon cancer and more than 4,000 patients with advanced colorectal cancer have been treated in clinical studies with oxaliplatin injection. The most common adverse reactions in patients with stage II or III colon cancer receiving adjuvant therapy were peripheral sensory neuropathy, neutropenia, thrombocytopenia, anemia, nausea, increase in transaminases and alkaline phosphatase, diarrhea, emesis, fatigue and stomatitis. The most common adverse reactions in previously untreated and treated patients were peripheral sensory neuropathies, fatigue, neutropenia, nausea, emesis, and diarrhea [see Warnings and Precautions (5)].
Combination Adjuvant Therapy with Oxaliplatin Injection and Infusional 5-fluorouracil/leucovorin in Patients with Colon Cancer
One thousand one hundred and eight patients with stage II or III colon cancer, who had undergone complete resection of the primary tumor, have been treated in a clinical study with oxaliplatin injection in combination with infusional 5-fluorouracil/leucovorin [see Clinical Studies (14)]. The incidence of grade 3 or 4 adverse reactions was 70% on the oxaliplatin injection combination arm, and 31% on the infusional 5-fluorouracil/leucovorin arm. The adverse reactions in this trial are shown in the tables below. Discontinuation of treatment due to adverse reactions occurred in 15% of the patients receiving oxaliplatin injection and infusional 5-fluorouracil/leucovorin. Both 5-fluorouracil/leucovorin and oxaliplatin injection are associated with gastrointestinal or hematologic adverse reactions. When oxaliplatin injection is administered in combination with infusional 5-fluorouracil/leucovorin, the incidence of these events is increased.
The incidence of death within 28 days of last treatment, regardless of causality, was 0.5% (n=6) in both the oxaliplatin injection combination and infusional 5-fluorouracil/leucovorin arms, respectively. Deaths within 60 days from initiation of therapy were 0.3% (n=3) in both the oxaliplatin injection combination and infusional 5-fluorouracil/leucovorin arms, respectively. On the oxaliplatin injection combination arm, 3 deaths were due to sepsis/neutropenic sepsis, 2 from intracerebral bleeding and one from eosinophilic pneumonia. On the 5-fluorouracil/leucovorin arm, one death was due to suicide, 2 from Steven-Johnson Syndrome (1 patient also had sepsis), 1 unknown cause, 1 anoxic cerebral infarction and 1 probable abdominal aorta rupture.
The following table provides adverse reactions reported in the adjuvant therapy colon cancer clinical trial [see Clinical Studies (14)] by body system and decreasing order of frequency in the oxaliplatin injection and infusional 5-fluorouracil/leucovorin arm for events with overall incidences ≥ 5% and for NCI grade 3/4 events with incidences ≥ 1%.

Table 3 - Adverse Reactions Reported in Patients with Colon Cancer receiving Adjuvant Treatment (≥5% of all patients and with ≥1% NCI Grade 3/4 events)
 | Oxaliplatin Injection + 5-FU/LV N=1108 |  | 5-FU/LV N=1111
Adverse reaction (WHO/Pref) | All Grades (%) | Grade 3/4 (%) | All Grades (%) | Grade 3/4 (%)
Any Event | 100 | 70 | 99 | 31
Allergy/Immunology
Allergic Reaction | 10 | 3 | 2 | <1
Constitutional Symptoms/Pain
Fatigue | 44 | 4 | 38 | 1
Abdominal Pain | 18 | 1 | 17 | 2
Dermatology/Skin
Skin Disorder | 32 | 2 | 36 | 2
Injection Site Reaction [Includes thrombosis related to the catheter] | 11 | 3 | 10 | 3
Gastrointestinal
Nausea | 74 | 5 | 61 | 2
Diarrhea | 56 | 11 | 48 | 7
Vomiting | 47 | 6 | 24 | 1
Stomatitis | 42 | 3 | 40 | 2
Anorexia | 13 | 1 | 8 | <1
Fever/Infection
Fever | 27 | 1 | 12 | 1
Infection | 25 | 4 | 25 | 3
Neurology
Overall Peripheral Sensory Neuropathy | 92 | 12 | 16 | <1

The following table provides adverse reactions reported in the adjuvant therapy colon cancer clinical trial [see Clinical Studies (14)] by body system and decreasing order of frequency in the oxaliplatin injection and infusional 5-fluorouracil/leucovorin arm for events with overall incidences ≥ 5% but with incidences <1% NCI grade 3/4 events.

Table 4 - Adverse Reactions Reported in Patients with Colon Cancer receiving Adjuvant Treatment (≥ 5% of all patients, but with <1% NCI Grade 3/4 events)
Adverse reaction (WHO/Pref) | Oxaliplatin Injection + 5-FU/LV N=1108 | 5-FU/LV N=1111
 | All Grades (%) | All Grades (%)
Allergy/Immunology
Rhinitis | 6 | 8
Constitutional Symptoms/Pain/Ocular/Visual
Epistaxis | 16 | 12
Weight Increase | 10 | 10
Conjunctivitis | 9 | 15
Headache | 7 | 5
Dyspnea | 5 | 3
Pain | 5 | 5
Lacrimation Abnormal | 4 | 12
Dermatology/Skin
Alopecia | 30 | 28
Gastrointestinal
Constipation | 22 | 19
Taste Perversion | 12 | 8
Dyspepsia | 8 | 5
Metabolic
Phosphate Alkaline increased | 42 | 20
Neurology
Sensory Disturbance | 8 | 1

Although specific events can vary, the overall frequency of adverse reactions was similar in men and women and in patients <65 and ≥65 years. However, the following grade 3/4 events were more common in females: diarrhea, fatigue, granulocytopenia, nausea and vomiting. In patients ≥65 years old, the incidence of grade 3/4 diarrhea and granulocytopenia was higher than in younger patients. Insufficient subgroup sizes prevented analysis of safety by race. The following additional adverse reactions, were reported in ≥2% and <5% of the patients in the oxaliplatin injection and infusional 5-fluorouracil/leucovorin combination arm (listed in decreasing order of frequency): pain, leukopenia, weight decrease, coughing.
The number of patients who developed secondary malignancies was similar; 62 in the oxaliplatin injection combination arm and 68 in the infusional 5-fluorouracil/leucovorin arm. An exploratory analysis showed that the number of deaths due to secondary malignancies was 1.96% in the oxaliplatin injection combination arm and 0.98% in infusional 5-fluorouracil/leucovorin arm. In addition, the number of cardiovascular deaths was 1.4% in the oxaliplatin injection combination arm as compared to 0.7% in the infusional 5-fluorouracil/leucovorin arm. Clinical significance of these findings is unknown.
Patients Previously Untreated for Advanced Colorectal Cancer
Two hundred and fifty-nine patients were treated in the oxaliplatin injection and 5-fluorouracil/leucovorin combination arm of the randomized trial in patients previously untreated for advanced colorectal cancer [see Clinical Studies (14)]. The adverse reaction profile in this study was similar to that seen in other studies and the adverse reactions in this trial are shown in the tables below.
Both 5-fluorouracil and oxaliplatin injection are associated with gastrointestinal and hematologic adverse reactions. When oxaliplatin injection is administered in combination with 5-fluorouracil, the incidence of these events is increased.
The incidence of death within 30 days of treatment in the previously untreated for advanced colorectal cancer study, regardless of causality, was 3% with the oxaliplatin injection and 5-fluorouracil/leucovorin combination, 5% with irinotecan plus 5-fluorouracil/leucovorin, and 3% with oxaliplatin injection plus irinotecan. Deaths within 60 days from initiation of therapy were 2.3% with the oxaliplatin injection and 5-fluorouracil/leucovorin combination, 5.1% with irinotecan plus 5-fluorouracil/leucovorin, and 3.1% with oxaliplatin injection plus irinotecan. The following table provides adverse reactions reported in the previously untreated for advanced colorectal cancer study [see Clinical Studies (14)] by body system and decreasing order of frequency in the oxaliplatin injection and 5-fluorouracil/leucovorin combination arm for events with overall incidences ≥5% and for grade 3/4 events with incidences ≥1%.

Table 5 – Adverse Reactions Reported in Patients Previously Untreated for Advanced Colorectal Cancer Clinical Trial (≥5% of all patients and with ≥1% NCI Grade 3/4 events)
 | Oxaliplatin Injection + 5-FU/LV N=259 |  | Irinotecan + 5-FU/LV N=256 |  | Oxaliplatin Injection + Irinotecan N=258
Adverse reaction (WHO/Pref) | All Grades (%) | Grade 3/4 (%) | All Grades (%) | Grade 3/4 (%) | All Grades (%) | Grade 3/4 (%)
Any Event | 99 | 82 | 98 | 70 | 99 | 76
Allergy/Immunology
Hypersensitivity | 12 | 2 | 5 | 0 | 6 | 1
Cardiovascular
Thrombosis | 6 | 5 | 6 | 6 | 3 | 3
Hypotension | 5 | 3 | 6 | 3 | 4 | 3
Constitutional Symptoms/Pain/Ocular/Visual
Fatigue | 70 | 7 | 58 | 11 | 66 | 16
Abdominal Pain | 29 | 8 | 31 | 7 | 39 | 10
Myalgia | 14 | 2 | 6 | 0 | 9 | 2
Pain | 7 | 1 | 5 | 1 | 6 | 1
Vision abnormal | 5 | 0 | 2 | 1 | 6 | 1
Neuralgia | 5 | 0 | 0 | 0 | 2 | 1
Dermatology/Skin
Skin reaction – hand/foot | 7 | 1 | 2 | 1 | 1 | 0
Injection site reaction | 6 | 0 | 1 | 0 | 4 | 1
Gastrointestinal
Nausea | 71 | 6 | 67 | 15 | 83 | 19
Diarrhea | 56 | 12 | 65 | 29 | 76 | 25
Vomiting | 41 | 4 | 43 | 13 | 64 | 23
Stomatitis | 38 | 0 | 25 | 1 | 19 | 1
Anorexia | 35 | 2 | 25 | 4 | 27 | 5
Constipation | 32 | 4 | 27 | 2 | 21 | 2
Diarrhea-colostomy | 13 | 2 | 16 | 7 | 16 | 3
Gastrointestinal NOS [Not otherwise specified] | 5 | 2 | 4 | 2 | 3 | 2
Hematology/Infection
Infection normal ANC [Absolute neutrophil count] | 10 | 4 | 5 | 1 | 7 | 2
Infection low ANC | 8 | 8 | 12 | 11 | 9 | 8
Lymphopenia | 6 | 2 | 4 | 1 | 5 | 2
Febrile neutropenia | 4 | 4 | 15 | 14 | 12 | 11
Hepatic/Metabolic/Laboratory/Renal
Hyperglycemia | 14 | 2 | 11 | 3 | 12 | 3
Hypokalemia | 11 | 3 | 7 | 4 | 6 | 2
Dehydration | 9 | 5 | 16 | 11 | 14 | 7
Hypoalbuminemia | 8 | 0 | 5 | 2 | 9 | 1
Hyponatremia | 8 | 2 | 7 | 4 | 4 | 1
Urinary frequency | 5 | 1 | 2 | 1 | 3 | 1
Neurology
Overall Neuropathy | 82 | 19 | 18 | 2 | 69 | 7
Paresthesias | 77 | 18 | 16 | 2 | 62 | 6
Pharyngo-laryngeal dysesthesias | 38 | 2 | 1 | 0 | 28 | 1
Neuro-sensory | 12 | 1 | 2 | 0 | 9 | 1
Neuro NOS | 1 | 0 | 1 | 0 | 1 | 0
Pulmonary
Cough | 35 | 1 | 25 | 2 | 17 | 1
Dyspnea | 18 | 7 | 14 | 3 | 11 | 2
Hiccups | 5 | 1 | 2 | 0 | 3 | 2

The following table provides adverse reactions reported in the previously untreated for advanced colorectal cancer study [see Clinical Studies (14)] by body system and decreasing order of frequency in the oxaliplatin injection and 5-fluorouracil/leucovorin combination arm for events with overall incidences ≥5% but with incidences <1% NCI Grade 3/4 events.

Table 6 - Adverse Reactions Reported in Patients Previously Untreated for Advanced Colorectal Cancer Clinical Trial (≥5% of all patients but with < 1% NCI Grade 3/4 events)
Adverse reaction (WHO/Pref) | Oxaliplatin Injection + 5-FU/LV N=259 | Irinotecan + 5-FU/LV N=256 | Oxaliplatin Injection + Irinotecan N=258
Adverse reaction (WHO/Pref) | All Grades (%) | All Grades (%) | All Grades (%)
Allergy/Immunology
Rash | 11 | 4 | 7
Rhinitis allergic | 10 | 6 | 6
Cardiovascular
Edema | 15 | 13 | 10
Constitutional Symptoms/Pain/Ocular/Visual
Headache | 13 | 6 | 9
Weight loss | 11 | 9 | 11
Epistaxis | 10 | 2 | 2
Tearing | 9 | 1 | 2
Rigors | 8 | 2 | 7
Dysphasia | 5 | 3 | 3
Sweating | 5 | 6 | 12
Arthralgia | 5 | 5 | 8
Dermatology/Skin
Alopecia | 38 | 44 | 67
Flushing | 7 | 2 | 5
Pruritis | 6 | 4 | 2
Dry Skin | 6 | 2 | 5
Gastrointestinal
Taste perversion | 14 | 6 | 8
Dyspepsia | 12 | 7 | 5
Flatulence | 9 | 6 | 5
Mouth Dryness | 5 | 2 | 3
Hematology/Infection
Fever normal ANC [Absolute neutrophil count] | 16 | 9 | 9
Hepatic/Metabolic/Laboratory/Renal
Hypocalcemia | 7 | 5 | 4
Elevated Creatinine | 4 | 4 | 5
Neurology
Insomnia | 13 | 9 | 11
Depression | 9 | 5 | 7
Dizziness | 8 | 6 | 10
Anxiety | 5 | 2 | 6

Adverse reactions were similar in men and women and in patients <65 and ≥65 years, but older patients may have been more susceptible to diarrhea, dehydration, hypokalemia, leukopenia, fatigue and syncope. The following additional adverse reactions, at least possibly related to treatment and potentially important, were reported in ≥2% and <5% of the patients in the oxaliplatin injection and 5-fluorouracil/leucovorin combination arm (listed in decreasing order of frequency): metabolic, pneumonitis, catheter infection, vertigo, prothrombin time, pulmonary, rectal bleeding, dysuria, nail changes, chest pain, rectal pain, syncope, hypertension, hypoxia, unknown infection, bone pain, pigmentation changes, and urticaria.
Previously Treated Patients with Advanced Colorectal Cancer
Four hundred and fifty patients (about 150 receiving the combination of oxaliplatin injection and 5-fluorouracil/leucovorin) were studied in a randomized trial in patients with refractory and relapsed colorectal cancer [see Clinical Studies (14)]. The adverse reaction profile in this study was similar to that seen in other studies and the adverse reactions in this trial are shown in the tables below. Thirteen percent of patients in the oxaliplatin injection and 5-fluorouracil/leucovorin combination arm and 18% in the 5-fluorouracil/leucovorin arm of the previously treated study had to discontinue treatment because of adverse effects related to gastrointestinal, or hematologic adverse reactions, or neuropathies. Both 5-fluorouracil and oxaliplatin injection are associated with gastrointestinal and hematologic adverse reactions. When oxaliplatin injection is administered in combination with 5-fluorouracil, the incidence of these events is increased.
The incidence of death within 30 days of treatment in the previously treated study, regardless of causality, was 5% with the oxaliplatin injection and 5-fluorouracil/leucovorin combination, 8% with oxaliplatin injection alone, and 7% with 5-fluorouracil/leucovorin. Of the 7 deaths that occurred on the oxaliplatin injection and 5-fluorouracil/leucovorin combination arm within 30 days of stopping treatment, 3 may have been treatment related, associated with gastrointestinal bleeding or dehydration.
The following table provides adverse reactions reported in the previously treated study [see Clinical Studies (14)] by body system and in decreasing order of frequency in the oxaliplatin injection and 5-fluorouracil/leucovorin combination arm for events with overall incidences ≥5% and for grade 3/4 events with incidences ≥1%. This table does not include hematologic and blood chemistry abnormalities; these are shown separately below.

Table 7 – Adverse Reactions Reported In Previously Treated Colorectal Cancer Clinical Trial (≥5% of all patients and with ≥1% NCI Grade 3/4 events)
 | 5-FU/LV (N = 142) |  | Oxaliplatin Injection (N = 153) |  | Oxaliplatin Injection + 5-FU/LV (N = 150)
Adverse reaction (WHO/Pref) | All Grades (%) | Grade 3/4 (%) | All Grades (%) | Grade 3/4 (%) | All Grades (%) | Grade 3/4 (%)
Any Event | 98 | 41 | 100 | 46 | 99 | 73
Cardiovascular
Dyspnea | 11 | 2 | 13 | 7 | 20 | 4
Coughing | 9 | 0 | 11 | 0 | 19 | 1
Edema | 13 | 1 | 10 | 1 | 15 | 1
Thromboembolism | 4 | 2 | 2 | 1 | 9 | 8
Chest Pain | 4 | 1 | 5 | 1 | 8 | 1
Constitutional Symptoms/Pain
Fatigue | 52 | 6 | 61 | 9 | 68 | 7
Back Pain | 16 | 4 | 11 | 0 | 19 | 3
Pain | 9 | 3 | 14 | 3 | 15 | 2
Dermatology/Skin
Injection Site Reaction | 5 | 1 | 9 | 0 | 10 | 3
Gastrointestinal
Diarrhea | 44 | 3 | 46 | 4 | 67 | 11
Nausea | 59 | 4 | 64 | 4 | 65 | 11
Vomiting | 27 | 4 | 37 | 4 | 40 | 9
Stomatitis | 32 | 3 | 14 | 0 | 37 | 3
Abdominal Pain | 31 | 5 | 31 | 7 | 33 | 4
Anorexia | 20 | 1 | 20 | 2 | 29 | 3
Gastroesophageal Reflux | 3 | 0 | 1 | 0 | 5 | 2
Hematology/Infection
Fever | 23 | 1 | 25 | 1 | 29 | 1
Febrile Neutropenia | 1 | 1 | 0 | 0 | 6 | 6
Hepatic/Metabolic/Laboratory/Renal
Hypokalemia | 3 | 1 | 3 | 2 | 9 | 4
Dehydration | 6 | 4 | 5 | 3 | 8 | 3
Neurology
Neuropathy | 17 | 0 | 76 | 7 | 74 | 7
Acute | 10 | 0 | 65 | 5 | 56 | 2
Persistent | 9 | 0 | 43 | 3 | 48 | 6

The following table provides adverse reactions reported in the previously treated study [see Clinical Studies (14)] by body system and in decreasing order of frequency in the oxaliplatin injection and 5-fluorouracil/leucovorin combination arm for events with overall incidences ≥5% but with incidences <1% NCI Grade 3/4 events.

Table 8 - Adverse Reactions Reported In Previously Treated Colorectal Cancer Clinical Trial (≥5% of all patients but with < 1% NCI Grade 3/4 events)
Adverse reaction (WHO/Pref) | 5-FU/LV (N = 142) | Oxaliplatin Injection (N = 153) | Oxaliplatin Injection + 5-FU/LV (N = 150)
Adverse reaction (WHO/Pref) | All Grades (%) | All Grades (%) | All Grades (%)
Allergy/Immunology
Rhinitis | 4 | 6 | 15
Allergic Reaction | 1 | 3 | 10
Rash | 5 | 5 | 9
Cardiovascular
Peripheral Edema | 11 | 5 | 10
Constitutional Symptoms/Pain/Ocular/Visual
Headache | 8 | 13 | 17
Arthralgia | 10 | 7 | 10
Epistaxis | 1 | 2 | 9
Abnormal Lacrimation | 6 | 1 | 7
Rigors | 6 | 9 | 7
Dermatology/Skin
Hand-Foot Syndrome | 13 | 1 | 11
Flushing | 2 | 3 | 10
Alopecia | 3 | 3 | 7
Gastrointestinal
Constipation | 23 | 31 | 32
Dyspepsia | 10 | 7 | 14
Taste Perversion | 1 | 5 | 13
Mucositis | 10 | 2 | 7
Flatulence | 6 | 3 | 5
Hepatic/Metabolic/Laboratory/Renal
Hematuria | 4 | 0 | 6
Dysuria | 1 | 1 | 6
Neurology
Dizziness | 8 | 7 | 13
Insomnia | 4 | 11 | 9
Pulmonary
Upper Resp Tract Infection | 4 | 7 | 10
Pharyngitis | 10 | 2 | 9
Hiccup | 0 | 2 | 5

Adverse reactions were similar in men and women and in patients <65 and ≥65 years, but older patients may have been more susceptible to dehydration, diarrhea, hypokalemia and fatigue. The following additional adverse reactions, at least possibly related to treatment and potentially important, were reported in ≥2% and <5% of the patients in the oxaliplatin injection and 5-fluorouracil/leucovorin combination arm (listed in decreasing order of frequency): anxiety, myalgia, erythematous rash, increased sweating, conjunctivitis, weight decrease, dry mouth, rectal hemorrhage, depression, ataxia, ascites, hemorrhoids, muscle weakness, nervousness, tachycardia, abnormal micturition frequency, dry skin, pruritus, hemoptysis, purpura, vaginal hemorrhage, melena, somnolence, pneumonia, proctitis, involuntary muscle contractions, intestinal obstruction, gingivitis, tenesmus, hot flashes, enlarged abdomen, urinary incontinence.
Hematologic Changes
The following tables list the hematologic changes occurring in ≥5% of patients, based on laboratory values and NCI grade, with the exception of those events occurring in adjuvant patients and anemia in the patients previously untreated for advanced colorectal cancer, respectively, which are based on AE reporting and NCI grade alone.

Table 9 - Adverse Hematologic Reactions in Patients with Colon Cancer Receiving Adjuvant Therapy (≥5% of patients)
Hematology Parameter | Oxaliplatin Injection + 5-FU/LV (N=1108) |  | 5-FU/LV (N=1111)
Hematology Parameter | All Grades (%) | Grade 3/4 (%) | All Grades (%) | Grade 3/4 (%)
Anemia | 76 | 1 | 67 | <1
Neutropenia | 79 | 41 | 40 | 5
Thrombocytopenia | 77 | 2 | 19 | <1

Table 10 – Adverse Hematologic Reactions in Patients Previously Untreated for Advanced Colorectal Cancer (≥5% of patients)
Hematology Parameter | Oxaliplatin Injection + 5-FU/LV N=259 |  | Irinotecan+ 5-FU/LV N=256 |  | Oxaliplatin Injection + Irinotecan N=258
Hematology Parameter | All Grades (%) | Grade 3/4 (%) | All Grades (%) | Grade 3/4 (%) | All Grades (%) | Grade 3/4 (%)
Anemia | 27 | 3 | 28 | 4 | 25 | 3
Leukopenia | 85 | 20 | 84 | 23 | 76 | 24
Neutropenia | 81 | 53 | 77 | 44 | 71 | 36
Thrombocytopenia | 71 | 5 | 26 | 2 | 44 | 4

Table 11 – Adverse Hematologic Reactions in Previously Treated Patients (≥5% of patients)
Hematology Parameter | 5-FU/LV (N=142) |  | Oxaliplatin Injection (N=153) |  | Oxaliplatin Injection + 5-FU/LV (N=150)
Hematology Parameter | All Grades (%) | Grade 3/4 (%) | All Grades (%) | Grade 3/4 (%) | All Grades (%) | Grade 3/4 (%)
Anemia | 68 | 2 | 64 | 1 | 81 | 2
Leukopenia | 34 | 1 | 13 | 0 | 76 | 19
Neutropenia | 25 | 5 | 7 | 0 | 73 | 44
Thrombocytopenia | 20 | 0 | 30 | 3 | 64 | 4

Thrombocytopenia and Bleeding
Thrombocytopenia was frequently reported with the combination of oxaliplatin injection and infusional 5-fluorouracil/leucovorin. The incidence of all hemorrhagic events in the adjuvant and previously treated patients was higher on the oxaliplatin injection combination arm compared to the infusional 5-fluorouracil/leucovorin arm. These events included gastrointestinal bleeding, hematuria, and epistaxis. In the adjuvant trial, two patients died from intracerebral hemorrhages.
The incidence of Grade 3/4 thrombocytopenia was 2% in adjuvant patients with colon cancer. In patients treated for advanced colorectal cancer the incidence of Grade 3/4 thrombocytopenia was 3 to 5%, and the incidence of these events was greater for the combination of oxaliplatin injection and 5-fluorouracil/leucovorin over the irinotecan plus 5-fluorouracil/leucovorin or 5-fluorouracil/leucovorin control groups. Grade 3/4 gastrointestinal bleeding was reported in 0.2% of adjuvant patients receiving oxaliplatin injection and 5-fluorouracil/leucovorin. In the previously untreated patients, the incidence of epistaxis was 10% in the oxaliplatin injection and 5-fluorouracil/leucovorin arm, and 2% and 1%, respectively, in the irinotecan plus 5-fluorouracil/leucovorin or irinotecan plus oxaliplatin injection arms.
Neutropenia
Neutropenia was frequently observed with the combination of oxaliplatin injection and 5-fluorouracil/leucovorin, with Grade 3 and 4 events reported in 29% and 12% of adjuvant patients with colon cancer, respectively. In the adjuvant trial, 3 patients died from sepsis/neutropenic sepsis. Grade 3 and 4 events were reported in 35% and 18% of the patients previously untreated for advanced colorectal cancer, respectively. Grade 3 and 4 events were reported in 27% and 17% of previously treated patients, respectively. In adjuvant patients the incidence of either febrile neutropenia (0.7%) or documented infection with concomitant grade 3/4 neutropenia (1.1%) was 1.8% in the oxaliplatin injection and 5-fluorouracil/leucovorin arm. The incidence of febrile neutropenia in the patients previously untreated for advanced colorectal cancer was 15% (3% of cycles) in the irinotecan plus 5-fluorouracil/leucovorin arm and 4% (less than 1% of cycles) in the oxaliplatin injection and 5-fluorouracil/leucovorin combination arm. Additionally, in this same population, infection with grade 3 or 4 neutropenia was 12% in the irinotecan plus 5-fluorouracil/leucovorin, and 8% in the oxaliplatin injection and 5-fluorouracil/leucovorin combination. The incidence of febrile neutropenia in the previously treated patients was 1% in the 5-fluorouracil/leucovorin arm and 6% (less than 1% of cycles) in the oxaliplatin injection and 5-fluorouracil/leucovorin combination arm.
Gastrointestinal
In patients receiving the combination of oxaliplatin injection plus infusional 5-fluorouracil/leucovorin for adjuvant treatment for colon cancer the incidence of Grade 3/4 nausea and vomiting was greater than those receiving infusional 5-fluorouracil/leucovorin alone (see table). In patients previously untreated for advanced colorectal cancer receiving the combination of oxaliplatin injection and 5-fluorouracil/leucovorin, the incidence of Grade 3 and 4 vomiting and diarrhea was less compared to irinotecan plus 5-fluorouracil/leucovorin controls (see table). In previously treated patients receiving the combination of oxaliplatin injection and 5-fluorouracil/leucovorin, the incidence of Grade 3 and 4 nausea, vomiting, diarrhea, and mucositis/stomatitis increased compared to 5-fluorouracil/leucovorin controls (see table).
The incidence of gastrointestinal adverse reactions in the previously untreated and previously treated patients appears to be similar across cycles. Premedication with antiemetics, including 5-HT3 blockers, is recommended. Diarrhea and mucositis may be exacerbated by the addition of oxaliplatin injection to 5-fluorouracil/leucovorin, and should be managed with appropriate supportive care. Since cold temperature can exacerbate acute neurological symptoms, ice (mucositis prophylaxis) should be avoided during the infusion of oxaliplatin injection.
Dermatologic
Oxaliplatin injection did not increase the incidence of alopecia compared to 5-fluorouracil/leucovorin alone. No complete alopecia was reported. The incidence of Grade 3/4 skin disorders was 2% in both the oxaliplatin injection plus infusional 5-fluorouracil/leucovorin and the infusional 5-fluorouracil/leucovorin alone arms in the adjuvant colon cancer patients. The incidence of hand-foot syndrome in patients previously untreated for advanced colorectal cancer was 2% in the irinotecan plus 5-fluorouracil/leucovorin arm and 7% in the oxaliplatin injection and 5-fluorouracil/leucovorin combination arm. The incidence of hand-foot syndrome in previously treated patients was 13% in the 5-fluorouracil/leucovorin arm and 11% in the oxaliplatin injection and 5-fluorouracil/leucovorin combination arm.
Intravenous Site Reactions
Extravasation, in some cases including necrosis, has been reported. Injection site reaction, including redness, swelling, and pain, has been reported.
Anticoagulation and Hemorrhage
There have been reports while on study and from postmarketing surveillance of prolonged prothrombin time and INR occasionally associated with hemorrhage in patients who received oxaliplatin injection plus 5-fluorouracil/leucovorin while on anticoagulants. Patients receiving oxaliplatin injection plus 5-fluorouracil/leucovorin and requiring oral anticoagulants may require closer monitoring.
Renal
About 5 to 10% of patients in all groups had some degree of elevation of serum creatinine. The incidence of Grade 3/4 elevations in serum creatinine in the oxaliplatin injection and 5-fluorouracil/leucovorin combination arm was 1% in the previously treated patients. Serum creatinine measurements were not reported in the adjuvant trial.
Hepatic
Hepatotoxicity (defined as elevation of liver enzymes) appears to be related to oxaliplatin injection combination therapy [see Warnings and Precautions (5.5)]. The following tables list the clinical chemistry changes associated with hepatic toxicity occurring in ≥5% of patients, based on adverse reactions reported and NCI CTC grade for adjuvant patients and patients previously untreated for advanced colorectal cancer, laboratory values and NCI CTC grade for previously treated patients.

Table 12 - Adverse Hepatic Reactions in Patients with Stage II or III Colon Cancer Receiving Adjuvant Therapy (≥5% of patients)
Hepatic Parameter | Oxaliplatin Injection + 5-FU/LV (N=1108) |  | 5-FU/LV (N=1111)
Hepatic Parameter | All Grades (%) | Grade 3/4 (%) | All Grades (%) | Grade 3/4 (%)
Increase in transaminases | 57 | 2 | 34 | 1
ALP increased | 42 | <1 | 20 | <1
Bilirubinaemia | 20 | 4 | 20 | 5

Table 13 – Adverse Hepatic – Clinical Chemistry Abnormalities in Patients Previously Untreated for Advanced Colorectal Cancer (≥5% of patients)
Clinical Chemistry | Oxaliplatin Injection + 5-FU/LV N=259 |  | Irinotecan + 5-FU/LV N=256 |  | Oxaliplatin Injection + Irinotecan N=258
Clinical Chemistry | All Grades (%) | Grade 3/4 (%) | All Grades (%) | Grade 3/4 (%) | All Grades (%) | Grade 3/4 (%)
ALT (SGPT-ALAT) | 6 | 1 | 2 | 0 | 5 | 2
AST (SGOT-ASAT) | 17 | 1 | 2 | 1 | 11 | 1
Alkaline Phosphatase | 16 | 0 | 8 | 0 | 14 | 2
Total Bilirubin | 6 | 1 | 3 | 1 | 3 | 2

Table 14 – Adverse Hepatic – Clinical Chemistry Abnormalities in Previously Treated Patients (≥5% of patients)
Clinical Chemistry | 5-FU/LV (N=142) |  | Oxaliplatin Injection (N=153) |  | Oxaliplatin Injection + 5-FU/LV (N=150)
Clinical Chemistry | All Grades (%) | Grade 3/4 (%) | All Grades (%) | Grade 3/4 (%) | All Grades (%) | Grade 3/4 (%)
ALT (SGPT-ALAT) | 28 | 3 | 36 | 1 | 31 | 0
AST (SGOT-ASAT) | 39 | 2 | 54 | 4 | 47 | 0
Total Bilirubin | 22 | 6 | 13 | 5 | 13 | 1

Thromboembolism
The incidence of thromboembolic events in adjuvant patients with colon cancer was 6% (1.8% grade 3/4) in the infusional 5-fluorouracil/leucovorin arm and 6% (1.2% grade 3/4) in the oxaliplatin injection and infusional 5-fluorouracil/leucovorin combined arm, respectively. The incidence was 6 and 9% of the patients previously untreated for advanced colorectal cancer and previously treated patients in the oxaliplatin injection and 5-fluorouracil/leucovorin combination arm, respectively.

6.2 Postmarketing Experience

The following adverse reactions have been identified during post-approval use of oxaliplatin injection. Because these reactions are reported voluntarily from a population of uncertain size, it is not always possible to reliably estimate their frequency or establish a causal relationship to drug exposure.

Body as a whole:

angioedema, anaphylactic shock

Cardiovascular disorders:

QT prolongation leading to ventricular arrhythmias including fatal Torsade de Pointes

Central and peripheral nervous system disorders:

loss of deep tendon reflexes, dysarthria, Lhermitte’s sign, cranial nerve palsies, fasciculations, convulsion, Reversible Posterior Leukoencephalopathy Syndrome (RPLS, also known as PRES).

Hearing and vestibular system disorders:

deafness

Infections:

septic shock, including fatal outcomes

Infusion reactions/hypersensitivity:

laryngospasm

Liver and Gastrointestinal system disorders:

severe diarrhea/vomiting resulting in hypokalemia, colitis (including Clostridium difficile diarrhea), metabolic acidosis; ileus; intestinal obstruction, pancreatitis; veno-occlusive disease of liver also known as sinusoidal obstruction syndrome, and perisinusoidal fibrosis which rarely may progress.

Musculoskeletal and connective tissue disorders

rhabdomyolysis, including fatal outcomes.

Platelet, bleeding, and clotting disorders:

immuno-allergic thrombocytopenia

prolongation of prothrombin time and of INR in patients receiving anticoagulants

Red Blood Cell disorders:

hemolytic uremic syndrome, immuno-allergic hemolytic anemia

Renal disorders:

Acute tubular necrosis, acute interstitial nephritis and acute renal failure.

Respiratory system disorders:

pulmonary fibrosis, and other interstitial lung diseases (sometimes fatal)

Vision disorders:

decrease of visual acuity, visual field disturbance, optic neuritis and transient vision loss (reversible following therapy discontinuation)

7 DRUG INTERACTIONS

No specific cytochrome P-450-based drug interaction studies have been conducted. No pharmacokinetic interaction between 85 mg/m^2 oxaliplatin injection and 5-fluorouracil/leucovorin has been observed in patients treated every 2 weeks. Increases of 5-fluorouracil plasma concentrations by approximately 20% have been observed with doses of 130 mg/m^2 oxaliplatin injection dosed every 3 weeks. Because platinum-containing species are eliminated primarily through the kidney, clearance of these products may be decreased by coadministration of potentially nephrotoxic compounds; although, this has not been specifically studied [see Clinical Pharmacology (12.3)].

8 USE IN SPECIFIC POPULATIONS

8.1 Pregnancy

Pregnancy Category D
Based on direct interaction with DNA, oxaliplatin injection may cause fetal harm when administered to a pregnant woman. There are no adequate and well-controlled studies of oxaliplatin injection in pregnant women. Reproductive toxicity studies in rats demonstrated adverse effects on fertility and embryo-fetal development at maternal doses that were below the recommended human dose based on body surface area. If this drug is used during pregnancy or if the patient becomes pregnant while taking this drug, the patient should be apprised of the potential hazard to the fetus. Women of childbearing potential should be advised to avoid becoming pregnant and use effective contraception while receiving treatment with oxaliplatin injection.
Pregnant rats were administered oxaliplatin at less than one-tenth the recommended human dose based on body surface area during gestation days 1 to 5 (pre-implantation), 6 to 10, or 11 to 16 (during organogenesis). Oxaliplatin caused developmental mortality (increased early resorptions) when administered on days 6 to 10 and 11 to 16 and adversely affected fetal growth (decreased fetal weight, delayed ossification) when administered on days 6 to 10. Administration of oxaliplatin to male and female rats prior to mating resulted in 97% post-implantation loss in animals that received approximately one-seventh the recommended human dose based on the body surface area.

8.3 Nursing Mothers

It is not known whether oxaliplatin injection or its derivatives are excreted in human milk. Because many drugs are excreted in human milk and because of the potential for serious adverse reactions in nursing infants from oxaliplatin injection, a decision should be made whether to discontinue nursing or discontinue the drug, taking into account the importance of the drug to the mother.

8.4 Pediatric Use

The effectiveness of oxaliplatin in children has not been established. Oxaliplatin has been tested in 2 Phase 1 and 2 Phase 2 trials in 235 patients ages 7 months to 22 years with solid tumors (see below) and no significant activity observed.
In a Phase 1/2 study, oxaliplatin was administered as a 2-hour intravenous infusion on Days 1, 8 and 15 every 4 weeks (1 cycle), for a maximum of 6 cycles, to 43 patients with refractory or relapsed malignant solid tumors, mainly neuroblastoma and osteosarcoma. Twenty eight pediatric patients in the Phase 1 study received oxaliplatin at 6 dose levels starting at 40 mg/m^2 with escalation to 110 mg/m^2. The dose limiting toxicity (DLT) was sensory neuropathy at the 110 mg/m^2 dose. Fifteen patients received oxaliplatin at a dose of 90 mg/m^2 intravenous in the Phase 2 portion of the study. At this dose, paresthesia (60%, G3/4: 7%), fever (40%, G3/4: 7%) and thrombocytopenia (40%, G3/4: 27%) were the main adverse reactions. No responses were observed.
In a second Phase 1 study, oxaliplatin was administered to 26 pediatric patients as a 2-hour intravenous infusion on day 1 every 3 weeks (1 cycle) at 5 dose levels starting at 100 mg/m^2 with escalation to 160 mg/m^2, for a maximum of 6 cycles. In a separate cohort, oxaliplatin 85 mg/m^2 was administered on day 1 every 2 weeks, for a maximum of 9 doses. Patients had metastatic or unresectable solid tumors mainly neuroblastoma and ganglioneuroblastoma. No responses were observed. The DLT was sensory neuropathy at the 160 mg/m^2 dose. Based on these studies, oxaliplatin 130 mg/m^2 as a 2-hour intravenous infusion on day 1 every 3 weeks (1 cycle) was used in subsequent Phase II studies. A dose of 85 mg/m^2 on day 1 every 2 weeks was also found to be tolerable.
In one Phase 2 study, 43 pediatric patients with recurrent or refractory embryonal CNS tumors received oxaliplatin 130 mg/m^2 every 3 weeks for a maximum of 12 months in absence of progressive disease or unacceptable toxicity. In patients < 10 kg the oxaliplatin dose used was 4.3 mg/kg. The most common adverse reactions reported were leukopenia (67%, G3/4: 12%), anemia (65%, G3/4: 5%), thrombocytopenia (65%, G3/4: 26%), vomiting (65%, G3/4: 7%), neutropenia (58%, G3/4: 16%) and sensory neuropathy (40%, G3/4: 5%). One partial response was observed.
In a second Phase 2 study, 123 pediatric patients with recurrent solid tumors, including neuroblastoma, osteosarcoma, Ewing sarcoma or peripheral PNET, ependymoma, rhabdomyosarcoma, hepatoblastoma, high grade astrocytoma, Brain stem glioma, low grade astrocytoma, malignant germ cell tumor and other tumors of interest received oxaliplatin 130 mg/m^2 every 3 weeks for a maximum of 12 months or 17 cycles. In patients < 12 months old the oxaliplatin dose used was 4.3 mg/kg. The most common adverse reactions reported were sensory neuropathy (52%, G3/4: 12%), thrombocytopenia (37%, G3/4: 17%), anemia (37%, G3/4: 9%), vomiting (26%, G3/4: 4%), ALT increased (24%, G3/4: 6%), AST increased (24%, G3/4: 2%), and nausea (23%, G3/4: 3%). Two partial responses were observed.
The pharmacokinetic parameters of ultrafiltrable platinum have been evaluated in 105 pediatric patients during the first cycle. The mean clearance in pediatric patients estimated by the population pharmacokinetic analysis was 4.7 L/h. The inter-patient variability of platinum clearance in pediatric cancer patients was 41%. Mean platinum pharmacokinetic parameters in ultrafiltrate were Cmax of 0.75 ± 0.24 mcg/mL, AUC0-48 of 7.52 ± 5.07 mcg·h/mL and AUCinf of 8.83 ± 1.57 mcg·h/mL at 85 mg/m² of oxaliplatin and Cmax of 1.1 ± 0.43 mcg/mL, AUC0-48 of 9.74 ± 2.52 mcg·h/mL and AUCinf of 17.3 ± 5.34 mcg·h/mL at 130 mg/m² of oxaliplatin.

8.5 Geriatric Use

No significant effect of age on the clearance of ultrafilterable platinum has been observed. In the adjuvant therapy colon cancer randomized clinical trial, [see Clinical Studies (14)] 723 patients treated with oxaliplatin injection and infusional 5-fluorouracil/leucovorin were <65 years and 400 patients were ≥65 years. A descriptive subgroup analysis demonstrated that the improvement in DFS for the oxaliplatin injection combination arm compared to the infusional 5-fluorouracil/leucovorin alone arm appeared to be maintained across genders. The effect of oxaliplatin injection in patients ≥65 years of age was not conclusive. Insufficient subgroup sizes prevented analysis by race. Patients ≥ 65 years of age receiving the oxaliplatin injection combination therapy experienced more grade 3 and 4 granulocytopenia than patients < 65 years of age (45% versus 39%).
In the previously untreated for advanced colorectal cancer randomized clinical trial [see Clinical Studies (14)] of oxaliplatin injection, 160 patients treated with oxaliplatin injection and 5-fluorouracil/leucovorin were < 65 years and 99 patients were ≥65 years. The same efficacy improvements in response rate, time to tumor progression, and overall survival were observed in the ≥65 year old patients as in the overall study population. In the previously treated for advanced colorectal cancer randomized clinical trial [see Clinical Studies (14)] of oxaliplatin injection, 95 patients treated with oxaliplatin injection and 5-fluorouracil/leucovorin were <65 years and 55 patients were ≥65 years. The rates of overall adverse reactions, including grade 3 and 4 events, were similar across and within arms in the different age groups in all studies. The incidence of diarrhea, dehydration, hypokalemia, leukopenia, fatigue and syncope were higher in patients ≥65 years old. No adjustment to starting dose was required in patients ≥65 years old.

8.6 Patients with Renal Impairment

The exposure (AUC) of unbound platinum in plasma ultrafiltrate tends to increase in renally impaired patients [see Pharmacokinetics (12.3)]. Caution and close monitoring should be exercised when oxaliplatin injection is administered to patients with renal impairment. The starting oxaliplatin injection dose does not need to be reduced in patients with mild (creatinine clearance = 50 to 80 mL/min) or moderate (creatinine clearance = 30 to 49 mL/min) renal impairment. However, the starting dose of oxaliplatin injection should be reduced in patients with severe renal impairment (creatinine clearance < 30 mL/min) [see Dosage and Administration (2.2)].

10 OVERDOSAGE

There is no known antidote for oxaliplatin injection overdose. In addition to thrombocytopenia, the anticipated complications of an oxaliplatin injection overdose include hypersensitivity reaction, myelosuppression, nausea, vomiting, diarrhea and neurotoxicity.
Several cases of overdoses have been reported with oxaliplatin injection. Adverse reactions observed were Grade 4 thrombocytopenia (<25,000/mm^3) without any bleeding, anemia, sensory neuropathy such as paresthesia, dysesthesia, laryngospasm and facial muscle spasms, gastrointestinal disorders such as nausea, vomiting, stomatitis, flatulence, abdomen enlarged and Grade 4 intestinal obstruction, Grade 4 dehydration, dyspnea, wheezing, chest pain, respiratory failure, severe bradycardia and death.
Patients suspected of receiving an overdose should be monitored, and supportive treatment should be administered. The maximum dose of oxaliplatin that has been administered in a single infusion is 825 mg.

11 DESCRIPTION

Oxaliplatin injection is an antineoplastic agent with the molecular formula C8H14N2O4Ptand the chemical name of cis-[(1R,2R)-1,2-cyclohexanediamine-N,N’] [oxalato(2-)-O,O’] platinum. Oxaliplatin is an organoplatinum complex in which the platinum atom is complexed with 1,2-diaminocyclohexane (DACH) and with an oxalate ligand as a leaving group.

The molecular weight is 397.3. Oxaliplatin is slightly soluble in water at 6 mg/mL, very slightly soluble in methanol, and practically insoluble in ethanol and acetone.
Oxaliplatin injection, USP is for intravenous use. Each mL of oxaliplatin injection contains 5 mg of oxaliplatin, USP. It is supplied as a sterile, preservative-free, aqueous solution in 50 mg/10 mL and 100 mg/20 mL vials. Water for injection is present as an inactive ingredient.

12 CLINICAL PHARMACOLOGY

12.1 Mechanism of Action

Oxaliplatin undergoes nonenzymatic conversion in physiologic solutions to active derivatives via displacement of the labile oxalate ligand. Several transient reactive species are formed, including monoaquo and diaquo DACH platinum, which covalently bind with macromolecules. Both inter- and intrastrand Pt-DNA crosslinks are formed. Crosslinks are formed between the N7 positions of two adjacent guanines (GG), adjacent adenine-guanines (AG), and guanines separated by an intervening nucleotide (GNG). These crosslinks inhibit DNA replication and transcription. Cytotoxicity is cell-cycle nonspecific. In vivo studies have shown antitumor activity of oxaliplatin against colon carcinoma. In combination with 5-fluorouracil, oxaliplatin exhibits in vitro and in vivo antiproliferative activity greater than either compound alone in several tumor models [HT29 (colon), GR (mammary), and L1210 (leukemia)].

12.3 Pharmacokinetics

The reactive oxaliplatin derivatives are present as a fraction of the unbound platinum in plasma ultrafiltrate. The decline of ultrafilterable platinum levels following oxaliplatin administration is triphasic, characterized by two relatively short distribution phases (t1/2α; 0.43 hours and t1/2β; 16.8 hours) and a long terminal elimination phase (t1/2γ; 391 hours). Pharmacokinetic parameters obtained after a single 2-hour intravenous infusion of oxaliplatin injection at a dose of 85 mg/m^2 expressed as ultrafilterable platinum were Cmax of 0.814 mcg/mL and volume of distribution of 440 L. Interpatient and intrapatient variability in ultrafilterable platinum exposure (AUC0-48hr) assessed over 3 cycles was moderate to low (23% and 6%, respectively). A pharmacodynamic relationship between platinum ultrafiltrate levels and clinical safety and effectiveness has not been established.
Distribution
At the end of a 2-hour infusion of oxaliplatin injection, approximately 15% of the administered platinum is present in the systemic circulation. The remaining 85% is rapidly distributed into tissues or eliminated in the urine. In patients, plasma protein binding of platinum is irreversible and is greater than 90%. The main binding proteins are albumin and gamma-globulins. Platinum also binds irreversibly and accumulates (approximately 2-fold) in erythrocytes, where it appears to have no relevant activity. No platinum accumulation was observed in plasma ultrafiltrate following 85 mg/m^2 every two weeks.
Metabolism
Oxaliplatin undergoes rapid and extensive nonenzymatic biotransformation. There is no evidence of cytochrome P450-mediated metabolism in vitro.
Up to 17 platinum-containing derivatives have been observed in plasma ultrafiltrate samples from patients, including several cytotoxic species (monochloro DACH platinum, dichloro DACH platinum, and monoaquo and diaquo DACH platinum) and a number of noncytotoxic, conjugated species.
Elimination
The major route of platinum elimination is renal excretion. At five days after a single 2-hour infusion of oxaliplatin injection, urinary elimination accounted for about 54% of the platinum eliminated, with fecal excretion accounting for only about 2%. Platinum was cleared from plasma at a rate (10 to 17 L/h) that was similar to or exceeded the average human glomerular filtration rate (GFR; 7.5 L/h). There was no significant effect of gender on the clearance of ultrafilterable platinum. The renal clearance of ultrafilterable platinum is significantly correlated with GFR.
Pharmacokinetics in Special Populations
Pediatric
[See Use In Specific Patient Populations (8.4)].
Renal Impairment
A study was conducted in 38 patients with advanced GI cancer and varying degrees of renal impairment. Patients in the normal (creatinine clearance (CrCL) > 80 mL/min, N = 11), mild (CrCL = 50 to 80 mL/min, N = 13), and moderate (CrCL = 30 to 49 mL/min, N = 10) groups were treated with 85 mg/m^2 oxaliplatin injection and those in the severe (CrCL < 30 mL/min, N = 4) group were treated with 65 mg/m^2 oxaliplatin injection. The mean AUC of unbound platinum was 40%, 95%, and 342% higher in the mild, moderate, and severe groups, respectively, than in the normal group. Mean Cmax of unbound platinum appeared to be similar among the normal, mild and moderate renal function groups, but was 38% higher in the severe group than in the normal group. Caution should be exercised in renally impaired patients [see Use in Specific Populations (8.6)]. The starting dose of oxaliplatin injection should be reduced in patients with severe renal impairment [see Dosage and Administration (2.2)].
Drug - Drug Interactions
No pharmacokinetic interaction between 85 mg/m^2 of oxaliplatin injection and infusional 5-fluorouracil has been observed in patients treated every 2 weeks, but increases of 5-fluorouracil plasma concentrations by approximately 20% have been observed with doses of 130 mg/m^2 of oxaliplatin injection administered every 3 weeks. In vitro, platinum was not displaced from plasma proteins by the following medications: erythromycin, salicylate, sodium valproate, granisetron, and paclitaxel. In vitro, oxaliplatin is not metabolized by, nor does it inhibit, human cytochrome P450 isoenzymes. No P450-mediated drug-drug interactions are therefore anticipated in patients. Since platinum-containing species are eliminated primarily through the kidney, clearance of these products may be decreased by coadministration of potentially nephrotoxic compounds, although this has not been specifically studied.

13 NONCLINICAL TOXICOLOGY

13.1 Carcinogenesis, Mutagenesis, Impairment of Fertility

Long-term animal studies have not been performed to evaluate the carcinogenic potential of oxaliplatin. Oxaliplatin was not mutagenic to bacteria (Ames test) but was mutagenic to mammalian cells in vitro (L5178Y mouse lymphoma assay). Oxaliplatin was clastogenic both in vitro (chromosome aberration in human lymphocytes) and in vivo (mouse bone marrow micronucleus assay).
In a fertility study, male rats were given oxaliplatin at 0, 0.5, 1, or 2 mg/kg/day for five days every 21 days for a total of three cycles prior to mating with females that received two cycles of oxaliplatin on the same schedule. A dose of 2 mg/kg/day (less than one-seventh the recommended human dose on a body surface area basis) did not affect pregnancy rate, but caused developmental mortality (increased early resorptions, decreased live fetuses, decreased live births) and delayed growth (decreased fetal weight).
Testicular damage, characterized by degeneration, hypoplasia, and atrophy, was observed in dogs administered oxaliplatin at 0.75 mg/kg/day x 5 days every 28 days for three cycles. A no effect level was not identified. This daily dose is approximately one-sixth of the recommended human dose on a body surface area basis.

14 CLINICAL STUDIES

14.1 Combination Adjuvant Therapy with Oxaliplatin Injection and Infusional 5-fluorouracil/leucovorin in Patients withColon Cancer

An international, multicenter, randomized study compared the efficacy and evaluated the safety of oxaliplatin injection in combination with an infusional schedule of 5-fluorouracil/leucovorin to infusional 5-fluorouracil/leucovorin

alone, in patients with stage II (Dukes’ B2) or III (Dukes’ C) colon cancer who had undergone complete resection of the primary tumor. The primary objective of the study was to compare the 3-year disease-free survival (DFS) in patients receiving oxaliplatin injection and infusional 5-fluorouracil/leucovorin

to those receiving 5-fluorouracil/leucovorin

alone. Patients were to be treated for a total of 6 months (i.e., 12 cycles). A total of 2246 patients were randomized; 1123 patients per study arm. Patients in the study had to be between 18 and 75 years of age, have histologically proven stage II (T3-T4 N0 M0; Dukes’ B2) or III (any T N1-2 M0; Dukes’ C) colon carcinoma (with the inferior pole of the tumor above the peritoneal reflection, i.e., ≥15 cm from the anal margin) and undergone (within 7 weeks prior to randomization) complete resection of the primary tumor without gross or microscopic evidence of residual disease. Patients had to have had no prior chemotherapy, immunotherapy or radiotherapy, and have an ECOG performance status of 0,1, or 2 (KPS ≥ 60%), absolute neutrophil count (ANC) > 1.5x10^9/L, platelets ≥100x10^9/L, serum creatinine ≤ 1.25 x ULN total bilirubin < 2 x ULN, AST/ALT < 2 x ULN and carcino-embryogenic antigen (CEA) < 10 ng/mL. Patients with preexisting peripheral neuropathy (NCI grade ≥ 1) were ineligible for this trial.
The following table shows the dosing regimens for the two arms of the study.

Table 15 - Dosing Regimens in Adjuvant Therapy Study
Treatment Arm | Dose | Regimen
Oxaliplatin injection + 5-FU/LV (FOLFOX4) (N =1123) | Day 1: Oxaliplatin Injection : 85 mg/m^2 (2-hour infusion) + LV: 200 mg/m^2 (2-hour infusion), followed by 5-FU: 400 mg/m^2 (bolus), 600 mg/m^2 (22-hour infusion) Day 2: LV: 200 mg/m^2 (2-hour infusion), followed by 5-FU: 400 mg/m^2 (bolus), 600 mg/m^2 (22-hour infusion) | every 2 weeks 12 cycles
5-FU/LV (N=1123) | Day 1: LV: 200 mg/m^2 (2-hour infusion), followed by 5-FU: 400 mg/m^2 (bolus), 600 mg/m^2 (22-hour infusion) Day 2: LV: 200 mg/m^2 (2-hour infusion), followed by 5-FU: 400 mg/m^2 (bolus), 600 mg/m^2 (22-hour infusion) | every 2 weeks 12 cycles

The following tables show the baseline characteristics and dosing of the patient population entered into this study. The baseline characteristics were well balanced between arms.

Table 16 - Patient Characteristics in Adjuvant Therapy Study
 | Oxaliplatin Injection + Infusional 5-FU/LV N=1123 | Infusional 5-FU/LV N=1123
Sex: Male (%) | 56.1 | 52.4
Female (%) | 43.9 | 47.6
Median age (years) | 61 | 60
<65 years of age (%) | 64.4 | 66.2
≥65 years of age (%) | 35.6 | 33.8
Karnofsky Performance Status (KPS) (%)
100 | 29.7 | 30.5
90 | 52.2 | 53.9
80 | 4.4 | 3.3
70 | 13.2 | 11.9
≤60 | 0.6 | 0.4
Primary site (%)
Colon including cecum | 54.6 | 54.4
Sigmoid | 31.9 | 33.8
Recto sigmoid | 12.9 | 10.9
Other including rectum | 0.6 | 0.9
Bowel obstruction (%)
Yes | 17.9 | 19.3
Perforation (%)
Yes | 6.9 | 6.9
Stage at Randomization (%)
II (T=3,4 N=0, M=0) | 40.1 | 39.9
III (T=any, N=1,2, M=0) | 59.6 | 59.3
IV (T=any, N=any, M=1) | 0.4 | 0.8
Staging – T (%)
T1 | 0.5 | 0.7
T2 | 4.5 | 4.8
T3 | 76 | 75.9
T4 | 19 | 18.5
Staging – N (%)
N0 | 40.2 | 39.9
N1 | 39.4 | 39.4
N2 | 20.4 | 20.7
Staging – M (%)
M1 | 0.4 | 0.8

Table 17 - Dosing in Adjuvant Therapy Study
 | Oxaliplatin Injection + Infusional 5-FU/LV N=1108 | Infusional 5-FU/LV N=1111
Median Relative Dose Intensity (%)
5-FU | 84.4 | 97.7
Oxaliplatin Injection | 80.5 | N/A
Median Number of Cycles | 12 | 12
Median Number of cycles with oxaliplatin injection | 11 | N/A

The following table and figures summarize the disease-free survival (DFS) results in the overall randomized population and in patients with stage II and III disease based on an ITT analysis. The median duration of follow-up was approximately 77 months.

Table 18 - Summary of DFS analysis - ITT analysis
Parameter | Oxaliplatin Injection + Infusional 5-FU/LV | Infusional 5-FU/LV
Overall
N | 1123 | 1123
Number of events – relapse or death (%) | 304 (27.1) | 360 (32.1)
Disease-free survival % [95% CI] [Disease-free survival at 5 years] | 73.3 [70.7, 76] | 67.4 [64.6, 70.2]
Hazard ratio [95% CI] [A hazard ratio of less than 1 favors Oxaliplatin Injection + Infusional 5-fluorouracil/leucovorin] | 0.8 [0.68, 0.93]
Stratified Logrank test | p=0.003
Stage III (Dukes’ C)
N | 672 | 675
Number of events –relapse or death (%) | 226 (33.6) | 271 (40.1)
Disease-free survival % [95% CI] | 66.4 [62.7, 70] | 58.9 [55.2, 62.7]
Hazard ratio [95% CI] | 0.78 [0.65, 0.93]
Logrank test | p=0.005
Stage II (Dukes’ B2)
N | 451 | 448
Number of events –relapse or death (%) | 78 (17.3) | 89 (19.9)
Disease-free survival % [95% CI] | 83.7 [80.2, 87.1] | 79.9 [76.2, 83.7]
Hazard ratio [95% CI] | 0.84 [0.62, 1.14]
Logrank test | p=0.258
Data cut off for disease free survival 1 June 2006

In the overall and stage III colon cancer populations DFS was statistically significantly improved in the oxaliplatin injection combination arm compared to infusional 5-fluorouracil/leucovorin alone. However, a statistically significant improvement in DFS was not noted in Stage II patients.
Figure 2 shows the DFS Kaplan-Meier curves for the comparison of oxaliplatin injection and infusional 5-fluorouracil/leucovorin

combination and infusional 5-fluorouracil/leucovorin

alone for the overall population (ITT analysis).
Figure 3 shows the DFS Kaplan-Meier curves for the comparison of oxaliplatin injection and infusional 5-fluorouracil/leucovorin

combination and infusional 5-fluorouracil/leucovorin

alone in Stage III patients.

Figure 2 - DFS Kaplan-Meier curves by treatment arm (cutoff: 1 June 2006) – ITT population
Figure 3 - DFS Kaplan-Meier curves by treatment arm in Stage III patients (cutoff: 1 June 2006) – ITT population
The following table summarizes the overall survival (OS) results in the overall randomized population and in patients with stage II and III disease, based on the ITT analysis.

Table 19 - Summary of OS analysis - ITT analysis
Parameter | Oxaliplatin Injection +Infusional 5-FU/LV | Infusional 5-FU/LV
Overall
N | 1123 | 1123
Number of death events (%) | 245 (21.8) | 283 (25.2)
Hazard ratio [A hazard ratio of less than 1 favors Oxaliplatin Injection + Infusional 5-fluorouracil/leucovorin] [95% CI] | 0.84 [0.71, 1]
Stage III (Dukes’ C)
N | 672 | 675
Number of death events (%) | 182 (27.1) | 220 (32.6)
Hazard ratio [95% CI] | 0.8 [0.65, 0.97]
Stage II (Dukes’ B2)
N | 451 | 448
Number of death events (%) | 63 (14) | 63 (14.1)
Hazard ratio [95% CI] | 1 [0.7, 1.41]
Data cut off for overall survival 16 January 2007

14.2 Combination Therapy with Oxaliplatin Injection and 5-fluorouracil/leucovorin in Patients Previously Untreated for Advanced Colorectal Cancer

A North American, multicenter, open-label, randomized controlled study was sponsored by the National Cancer Institute (NCI) as an intergroup study led by the North Central Cancer Treatment Group (NCCTG). The study had 7 arms at different times during its conduct, four of which were closed due to either changes in the standard of care, toxicity, or simplification. During the study, the control arm was changed to irinotecan plus 5-fluorouracil/leucovorin. The results reported below compared the efficacy and safety of two experimental regimens, oxaliplatin injection in combination with infusional 5-fluorouracil/leucovorinand a combination of oxaliplatin injection plus irinotecan, to an approved control regimen of irinotecan plus 5-fluorouracil/leucovorinin 795 concurrently randomized patients previously untreated for locally advanced or metastatic colorectal cancer. After completion of enrollment, the dose of irinotecan plus 5-fluorouracil/leucovorinwas decreased due to toxicity. Patients had to be at least 18 years of age, have known locally advanced, locally recurrent, or metastatic colorectal adenocarcinoma not curable by surgery or amenable to radiation therapy with curative intent, histologically proven colorectal adenocarcinoma, measurable or evaluable disease, with an ECOG performance status 0, 1, or 2. Patients had to have granulocyte count ≥ 1.5 x 10^9/L, platelets ≥ 100 x 10^9/L, hemoglobin ≥9 gm/dL, creatinine ≤ 1.5 x ULN, total bilirubin ≤ 1.5 mg/dL, AST ≤ 5 x ULN, and alkaline phosphatase ≤ 5 x ULN. Patients may have received adjuvant therapy for resected Stage II or III disease without recurrence within 12 months. The patients were stratified for ECOG performance status (0, 1 vs. 2), prior adjuvant chemotherapy (yes vs. no), prior immunotherapy (yes vs. no), and age (<65 vs. ≥65 years). Although no post study treatment was specified in the protocol, 65 to 72% of patients received additional post study chemotherapy after study treatment discontinuation on all arms. Fifty-eight percent of patients on the oxaliplatin injection plus 5-fluorouracil/leucovorinarm received an irinotecan-containing regimen and 23% of patients on the irinotecan plus 5-fluorouracil/leucovorinarm received oxaliplatin-containing regimens. Oxaliplatin was not commercially available during the trial.

The following table presents the dosing regimens of the three arms of the study.

Table 20 – Dosing Regimens in Patients Previously Untreated for Advanced Colorectal Cancer Clinical Trial
Treatment Arm | Dose | Regimen
Oxaliplatin Injection + 5-FU/LV (FOLFOX4) (N=267) | Day 1: Oxaliplatin Injection: 85 mg/m^2 (2-hour infusion) + LV 200 mg/m^2 (2-hour infusion), followed by 5-FU: 400 mg/m^2 (bolus), 600 mg/m^2 (22-hour infusion) Day 2: LV 200 mg/m^2 (2-hour infusion), followed by 5-FU: 400 mg/m^2 (bolus), 600 mg/m^2 (22-hour infusion) | every 2 weeks
Irinotecan + 5-FU/LV (IFL) (N=264) | Day 1: irinotecan 125 mg/m^2 as a 90–min infusion + LV 20 mg/m^2 as a 15-min infusion or intravenouspush, followed by 5-FU 500 mg/m^2intravenousbolus weekly x 4 | every 6 weeks
Oxaliplatin Injection + Irinotecan (IROX) (N=264) | Day 1: oxaliplatin injection : 85 mg/m^2 intravenous(2-hour infusion) + irinotecan 200 mg/m^2 intravenousover 30 minutes | every 3 weeks

The following table presents the demographics of the patient population entered into this study.

Table 21 – Patient Demographics in Patients Previously Untreated for Advanced Colorectal Cancer Clinical Trial
 | Oxaliplatin Injection + 5-FU/LV N=267 | Irinotecan + 5-FU/LV N=264 | Oxaliplatin Injection + Irinotecan N=264
Sex: Male (%) | 58.8 | 65.2 | 61
Female (%) | 41.2 | 34.8 | 39
Median age (years) | 61 | 61 | 61
<65 years of age (%) | 61 | 62 | 63
≥65 years of age (%) | 39 | 38 | 37
ECOG (%)
0 to 1 | 94.4 | 95.5 | 94.7
2 | 5.6 | 4.5 | 5.3
Involved organs (%)
Colon only | 0.7 | 0.8 | 0.4
Liver only | 39.3 | 44.3 | 39
Liver + other | 41.2 | 38.6 | 40.9
Lung only | 6.4 | 3.8 | 5.3
Other (including lymph nodes) | 11.6 | 11 | 12.9
Not reported | 0.7 | 1.5 | 1.5
Prior radiation (%) | 3 | 1.5 | 3
Prior surgery (%) | 74.5 | 79.2 | 81.8
Prior adjuvant (%) | 15.7 | 14.8 | 15.2

The length of a treatment cycle was 2 weeks for the oxaliplatin injection and 5-fluorouracil/leucovorin regimen; 6 weeks for the irinotecan plus 5-fluorouracil/leucovorin regimen; and 3 weeks for the oxaliplatin injection plus irinotecan regimen. The median number of cycles administered per patient was 10 (23.9 weeks) for the oxaliplatin injection and 5-fluorouracil/leucovorinregimen, 4 (23.6 weeks) for the irinotecan plus 5-fluorouracil/leucovorinregimen, and 7 (21 weeks) for the oxaliplatin injection plus irinotecan regimen. Patients treated with the oxaliplatin injection and 5-fluorouracil/leucovorincombination had a significantly longer time to tumor progression based on investigator assessment, longer overall survival, and a significantly higher confirmed response rate based on investigator assessment compared to patients given irinotecan plus 5-fluorouracil/leucovorin. The following table summarizes the efficacy results.

Table 22 – Summary of Efficacy
 | Oxaliplatin Injection + 5-FU/LV N=267 | Irinotecan + 5-FU/LV N=264 | Oxaliplatin Injection + Irinotecan N=264
Survival (ITT)
Number of deaths N (%) | 155 (58.1) | 192 (72.7) | 175 (66.3)
Median survival (months) | 19.4 | 14.6 | 17.6
Hazard Ratio and (95% confidence interval) | 0.65 (0.53 to 0.8) [Compared to irinotecan plus 5-fluorouracil/leucovorin (IFL) arm]
P-value | <0.0001 | - | -
TTP (ITT, investigator assessment)
Percentage of progressors | 82.8 | 81.8 | 89.4
Median TTP (months) | 8.7 | 6.9 | 6.5
Hazard Ratio and (95% confidence interval) [A hazard ratio of less than 1 favors oxaliplatin injection + Infusional 5-fluorouracil/leucovorin] | 0.74 (0.61 to 0.89)
P-value | 0.0014 | - | -
Response Rate (investigator assessment) [Based on all patients with measurable disease at baseline]
Patients with measurable disease | 210 | 212 | 215
Complete response N (%) | 13 (6.2) | 5 (2.4) | 7 (3.3)
Partial response N (%) | 82 (39) | 64 (30.2) | 67 (31.2)
Complete and partial response N (%) | 95 (45.2) | 69 (32.5) | 74 (34.4)
95% confidence interval | (38.5 to 52) | (26.2 to 38.9) | (28.1 to 40.8)
P-value | 0.008 | - | -
The numbers in the response rate and TTP analysis are based on unblinded investigator assessment.

Figure 4 illustrates the Kaplan-Meier survival curves for the comparison of oxaliplatin injection and 5-fluorouracil/leucovorincombination and oxaliplatin injection plus irinotecan to irinotecan plus 5-fluorouracil/leucovorin.

Figure 4- Kaplan-Meier Overall Survival by treatment arm

A descriptive subgroup analysis demonstrated that the improvement in survival for oxaliplatin injection plus 5-fluorouracil/leucovorincompared to irinotecan plus 5-fluorouracil/leucovorin appeared to be maintained across age groups, prior adjuvant therapy, and number of organs involved. An estimated survival advantage in oxaliplatin injection plus 5-fluorouracil/leucovorinversus irinotecan plus 5-fluorouracil/leucovorinwas seen in both genders; however it was greater among women than men. Insufficient subgroup sizes prevented analysis by race.

14.3 Combination Therapy with Oxaliplatin Injection and 5-fluorouracil/leucovorin in Previously Treated Patients with Advanced Colorectal Cancer

A multicenter, open-label, randomized, three-arm controlled study was conducted in the US and Canada comparing the efficacy and safety of oxaliplatin injection in combination with an infusional schedule of 5-fluorouracil/leucovorin

to the same dose and schedule of 5-fluorouracil/leucovorin

alone and to single agent oxaliplatin in patients with advanced colorectal cancer who had relapsed/progressed during or within 6 months of first-line therapy with bolus 5-fluorouracil/leucovorin

and irinotecan. The study was intended to be analyzed for response rate after 450 patients were enrolled. Survival will be subsequently assessed in all patients enrolled in the completed study. Accrual to this study is complete, with 821 patients enrolled. Patients in the study had to be at least 18 years of age, have unresectable, measurable, histologically proven colorectal adenocarcinoma, with a Karnofsky performance status >50%. Patients had to have SGOT(AST) and SGPT(ALT) ≤2x the institution’s upper limit of normal (ULN), unless liver metastases were present and documented at baseline by CT or MRI scan, in which case ≤5x ULN was permitted. Patients had to have alkaline phosphatase ≤2x the institution’s ULN, unless liver metastases were present and documented at baseline by CT or MRI scan, in which cases ≤5x ULN was permitted. Prior radiotherapy was permitted if it had been completed at least 3 weeks before randomization.
The dosing regimens of the three arms of the study are presented in the table below.

Table 23 – Dosing Regimens in Refractory and Relapsed Colorectal Cancer Clinical Trial
Treatment Arm | Dose | Regimen
Oxaliplatin Injection + 5-FU/LV (N =152) | Day 1: Oxaliplatin Injection: 85 mg/m^2 (2-hour infusion) + LV 200 mg/m^2 (2-hour infusion), followed by 5-FU: 400 mg/m^2 (bolus), 600 mg/m^2 (22-hour infusion) Day 2: LV 200 mg/m^2 (2-hour infusion), followed by 5-FU: 400 mg/m^2 (bolus), 600 mg/m^2 (22-hour infusion) | every 2 weeks
5-FU/LV (N=151) | Day 1: LV 200 mg/m^2 (2-hour infusion), followed by 5-FU: 400 mg/m^2 (bolus), 600 mg/m^2 (22-hour infusion) Day 2: LV 200 mg/m^2 (2-hour infusion), followed by 5-FU: 400 mg/m^2 (bolus), 600 mg/m^2 (22-hour infusion) | every 2 weeks
Oxaliplatin Injection (N=156) | Day 1: Oxaliplatin Injection 85 mg/m^2 (2-hour infusion) | every 2 weeks

Patients entered into the study for evaluation of response must have had at least one unidimensional lesion measuring ≥20mm using conventional CT or MRI scans, or ≥10mm using a spiral CT scan. Tumor response and progression were assessed every 3 cycles (6 weeks) using the Response Evaluation Criteria in Solid Tumors (RECIST) until radiological documentation of progression or for 13 months following the first dose of study drug(s), whichever came first. Confirmed responses were based on two tumor assessments separated by at least 4 weeks.
The demographics of the patient population entered into this study are shown in the table below.

Table 24 – Patient Demographics in Refractory and Relapsed Colorectal Cancer Clinical Trial
 | 5-FU/LV (N = 151) | Oxaliplatin Injection (N = 156) | Oxaliplatin Injection + 5-FU/LV (N = 152)
Sex: Male (%) | 54.3 | 60.9 | 57.2
Female (%) | 45.7 | 39.1 | 42.8
Median age (years) | 60 | 61 | 59
Range | 21 to 80 | 27 to 79 | 22 to 88
Race (%)
Caucasian | 87.4 | 84.6 | 88.8
Black | 7.9 | 7.1 | 5.9
Asian | 1.3 | 2.6 | 2.6
Other | 3.3 | 5.8 | 2.6
KPS (%)
70 to 100 | 94.7 | 92.3 | 95.4
50 to 60 | 2.6 | 4.5 | 2
Not reported | 2.6 | 3.2 | 2.6
Prior radiotherapy (%) | 25.2 | 19.2 | 25
Prior pelvic radiation (%) | 18.5 | 13.5 | 21.1
Number of metastatic sites (%)
1 | 27.2 | 31.4 | 25.7
≥2 | 72.2 | 67.9 | 74.3
Liver involvement (%)
Liver only | 22.5 | 25.6 | 18.4
Liver + other | 60.3 | 59 | 53.3

The median number of cycles administered per patient was 6 for the oxaliplatin injection and 5-fluorouracil/leucovorin

combination and 3 each for 5-fluorouracil/leucovorin

alone and oxaliplatin injection alone.
Patients treated with the combination of oxaliplatin injection and 5-fluorouracil/leucovorin

had an increased response rate compared to patients given 5-fluorouracil/leucovorin or oxaliplatin alone. The efficacy results are summarized in the tables below.

Table 25 - Response Rates (ITT Analysis)
Best Response | 5-FU/LV (N=151) | Oxaliplatin Injection (N=156) | Oxaliplatin Injection + 5-FU/LV (N=152)
CR | 0 | 0 | 0
PR | 0 | 2 (1%) | 13 (9%)
p-value | 0.0002 for 5-FU/LV vs. Oxaliplatin Injection + 5-FU/LV
95%CI | 0 to 2.4% | 0.2 to 4.6% | 4.6 to 14.2%

Table 26 - Summary of Radiographic Time to Progression [This is not an ITT analysis. Events were limited to radiographic disease progression documented by independent review of radiographs. Clinical progression was not included in this analysis, and 18% of patients were excluded from the analysis based on unavailability of the radiographs for independent review.]
Arm | 5-FU/LV (N=151) | Oxaliplatin Injection (N=156) | Oxaliplatin Injection + 5-FU/LV (N=152)
No. of Progressors | 74 | 101 | 50
No. of patients with no radiological evaluation beyond baseline | 22 (15%) | 16 (10%) | 17 (11%)
Median TTP (months) | 2.7 | 1.6 | 4.6
95% CI | 1.8 to 3 | 1.4 to 2.7 | 4.2 to 6.1

At the time of the interim analysis 49% of the radiographic progression events had occurred. In this interim analysis an estimated 2-month increase in median time to radiographic progression was observed compared to 5-fluorouracil/leucovorin

alone.
Of the 13 patients who had tumor response to the combination of oxaliplatin injection and 5-fluorouracil/leucovorin, 5 were female and 8 were male, and responders included patients <65 years old and ≥65 years old. The small number of non-Caucasian participants made efficacy analyses in these populations uninterpretable.

15 REFERENCES

1. NIOSH Alert: Preventing occupational exposures to antineoplastic and other hazardous drugs in healthcare settings. 2004. U.S. Department of Health and Human Services, Public Health Service, Centers for Disease Control and Prevention, National Institute for Occupational Safety and Health, DHHS (NIOSH) Publication No. 2004-165.
2. OSHA Technical Manual, TED 1-0.15A, Section VI: Chapter 2. Controlling Occupational Exposure to Hazardous Drugs. OSHA, 1999. http://www.osha.gov/dts/osta/otm/otm_vi/otm_vi_2.html
3. American Society of Health-System Pharmacists. (2006) ASHP Guidelines on Handling Hazardous Drugs.
4. Polovich, M., White, J. M., & Kelleher, L.O. (eds.) 2005. Chemotherapy and biotherapy guidelines and recommendations for practice (2nd. ed.) Pittsburgh, PA: Oncology Nursing Society.

16 HOW SUPPLIED/STORAGE AND HANDLING

16.1 How Supplied

Oxaliplatin injection, USP is supplied in clear, glass, single-use vials with gray elastomeric stoppers and aluminum flip-off seals containing 50 mg/10 mL or 100 mg/20 mL of oxaliplatin, USP as a sterile, preservative-free, aqueous solution at a concentration of 5 mg/mL. Water for Injection, USP is present as an inactive ingredient.
NDC 47335-046-40: 50 mg/10 mL single-use vial with parrot green flip-off seal individually packaged in a carton.
NDC 47335-047-40: 100 mg/20 mL single-use vial with golden brown flip-off seal individually packaged in a carton.

16.2 Storage

Store at 20° to 25°C (68° to 77°F); excursions permitted between 15° and 30°C (59° and 86°F) [see USP Controlled Room Temperature]. Do not freeze and protect from light (keep in original outer carton).

16.3 Handling and Disposal

As with other potentially toxic anticancer agents, care should be exercised in the handling and preparation of infusion solutions prepared from oxaliplatin injection. The use of gloves is recommended. If a solution of oxaliplatin injection contacts the skin, wash the skin immediately and thoroughly with soap and water. If oxaliplatin injection contacts the mucous membranes, flush thoroughly with water.
Procedures for the handling and disposal of anticancer drugs should be considered. Several guidelines on the subject have been published [see References (15)]. There is no general agreement that all of the procedures recommended in the guidelines are necessary or appropriate.

17 PATIENT COUNSELING INFORMATION

Advise patients:

- To expect side effects of oxaliplatin injection, particularly its neurologic effects, both the acute, reversible effects and the persistent neurosensory toxicity. Patients should be informed that the acute neurosensory toxicity may be precipitated or exacerbated by exposure to cold or cold objects.
- To avoid cold drinks, use of ice, and should cover exposed skin prior to exposure to cold temperature or cold objects.
- Of the risk of low blood cell counts and to contact their physician immediately should fever, particularly if associated with persistent diarrhea, or evidence of infection develop.
- To contact their physician if persistent vomiting, diarrhea, signs of dehydration, cough or breathing difficulties occur, or signs of allergic reaction appear.
- To exercise caution when driving and using machines. No studies on the effects of the ability to operate cars and machines have been performed; however, oxaliplatin treatment resulting in an increase risk of dizziness, nausea and vomiting, and other neurologic symptoms that affect gait and balance may lead to a minor or moderate influence on the ability to drive and use machines.
- Of the potential effects of vision abnormalities, in particular transient vision loss (reversible following therapy discontinuation), which may affect patients' ability to drive and use machines.

FDA-Approved Patient Labeling

Patient Information
Oxaliplatin (ox-Al-ah-platin) Injection, USP

for intravenous use
Read this Patient Information leaflet carefully before you start receiving oxaliplatin injection. There may be new information. It will help you learn more about oxaliplatin injection. This leaflet does not take the place of talking to your doctor about your medical condition or your treatment. Ask your doctor about any questions you have.

What is the most important information I should know about oxaliplatin injection?

Oxaliplatin can cause serious allergic reactions, including allergic reactions that can lead to death. Oxaliplatin injection is a platinum base medicine. Serious allergic reactions including death can happen in people who take oxaliplatin injection and who have had previous allergic reactions to platinum medicines. Serious allergic reactions can happen within a few minutes of your infusion or any time during your treatment with oxaliplatin injection.

Get emergency help right away if you:

- have trouble breathing.
- feel like your throat is closing up.

Call your doctor right away if you have any of the following signs or symptoms of an allergic reaction:

- rash
- flushed face
- hives
- itching
- swelling of your lips or tongue
- sudden cough
- dizziness or feel faint
- sweating
- chest pain

See “What are the possible side effects of oxaliplatin injection?” for information about other serious side effects.

What is oxaliplatin injection?

Oxaliplatin injection is an anti-cancer (chemotherapy) medicine that is used with other anti-cancer medicines called 5-fluorouracil and leucovorin to treat people with:

- stage III colon cancer after surgery to remove the tumor
- advanced colon or rectal cancer (colorectal cancer).

It is not known if oxaliplatin injection is effective in children.

Who should not receive oxaliplatin injection?

Do not receive oxaliplatin injection if you are allergic to any of the ingredients in oxaliplatin injection or other medicines that contain platinum. See the end of this leaflet for a complete list of the ingredients oxaliplatin injection.

Ask your doctor if you are not sure if you take a medicine that contains platinum.

What should I tell my doctor before receiving oxaliplatin injection?

Before receiving oxaliplatin injection, tell your doctor about all of your medical conditions, including if you:

- have an infection
- have lung, liver, or kidney problems
- have or had heart problems such as an abnormal heart test called an electrocardiogram (ECG or EKG), a condition called long QT syndrome, an irregular or slow heartbeat, or a family history of heart problems.
- have had changes in the level of certain blood salt (electrolytes) levels, including potassium, magnesium, and calcium
- are pregnant or plan to become pregnant. Oxaliplatin injection may harm your unborn baby. Females who are able to become pregnant should avoid becoming pregnant and should use effective birth control during treatment with oxaliplatin injection.
- are breastfeeding or plan to breastfeed. It is not known if oxaliplatin passes into your breast milk. You and your doctor should decide if you will receive oxaliplatin injection or breastfeed. You should not do both.

Tell your doctor about all the medicines you take, including prescription and over-the-counter medicines, vitamins, and herbal supplements.

Know the medicines you take. Keep a list of them and show it to your doctor and pharmacist when you get a new medicine.

How will I receive oxaliplatin injection?

- Oxaliplatin injection is given to you into your vein through an intravenous (IV) tube.
- Your doctor will prescribe oxaliplatin injection in a dose that is right for you.
- Your doctor may change how often you receive oxaliplatin injection, your dose, or how long your infusion will take.
- You and your doctor will decide how many oxaliplatin injection treatments you will receive.
- It is very important that you do exactly what your doctor and nurse tell you to do.
- Some medicines may be given to you before oxaliplatin injection to help prevent nausea and vomiting.
- Each treatment course is given to you over 2 days. You will receive oxaliplatin injection on the first day only.
- There are usually 14 days between each chemotherapy treatment course.
- It is important for you to keep all of your medical appointments. Call your doctor if you miss an appointment. There may be special instructions for you.

Treatment Day 1:

- Oxaliplatin injection and leucovorin will be given through a thin plastic tube into a vein (intravenous infusion or IV) and given for 2 hours. You will be watched by a healthcare provider during this time.
- Right after the oxaliplatin injection and leucovorin are given, 2 doses of 5-fluorouracil will be given. The first dose is given right away into your IV tube. The second dose will be given into your IV tube over the next 22 hours, using a pump device.

Treatment Day 2:

You will not get oxaliplatin injection on Day 2. Leucovorin and 5-fluorouracil will be given the same way as on Day 1.

The 5-fluorouracil will be given through your IV with a pump. If you have any problems with the pump or the tube, call your doctor, your nurse, or the person who is responsible for your pump. Do not let anyone other than a healthcare provider touch your infusion pump or tubing.

What should I avoid while receiving oxaliplatin injection?

- Avoid cold temperatures and cold objects. Cover your skin if you go outdoors in cold temperatures.
- Do not drink cold drinks or use ice cubes in drinks.
- Do not put ice or ice packs on your body.
- Oxaliplatin injection can cause dizziness, vision problems, or vision loss that can affect your ability to drive or use machines. You should not drive or operate machinery if you develop these symptoms while receiving oxaliplatin injection.

See “How can I reduce the side effects caused by cold temperatures?” for more information.

Talk with your doctor and nurse about your level of activity during treatment with oxaliplatin injection. Follow their instructions.

What are the possible side effects of oxaliplatin injection?

Oxaliplatin injection can cause serious side effects, including:

- See “What is the most important information I should know about oxaliplatin injection?”
- Nerve problems. Oxaliplatin injection can affect how your nerves work and make you feel. Nerve problems may happen with the first treatment or within two days after your treatment of oxaliplatin injection. Nerve problems may last a short time (acute) or may become persistent. Symptoms may improve after stopping treatment with oxaliplatin injection. Exposure to cold or cold objects may cause or worsen nerve problems. Tell your doctor right away if you get any signs of nerve problems, including:

o very sensitive to cold temperatures and cold objects

o trouble breathing, swallowing, or saying words, jaw tightness, odd feelings in your tongue, or chest pressure

o pain, tingling, burning (pins and needles, numb feeling) in your hands, feet, or around your mouth or throat, which may cause problems walking or performing activities of daily living.

For information on ways to lessen or help with the nerve problems, see the end of this leaflet, “How can I reduce the side effects caused by cold temperatures?”

- Reversible Posterior Leukoencephalopathy (RPLS). RPLS is a rare condition that affects the brain.

Tell your doctor right away if you have any of the following signs and symptoms of RPLS:

o headache

o confusion or a change in the way you think

o seizures

o vision problems, such as blurriness or vision loss

- Low white blood cell counts (neutropenia). Oxaliplatin injection can cause low white blood cells counts. Low blood cell counts are common with oxaliplatin injection and can lead to serious infection and death. Tell your doctor right away if you have a fever greater than 100.9°F (38.3°C) or a prolonged fever greater than 100.4°F (38°C) for more than one hour (febrile neutropenia). Call your doctor right away if you get any of the following signs of infection:

o chills or shivering

o pain on swallowing

o sore throat

o cough that brings up mucus

o burning or pain on urination

o redness or swelling at intravenous site

o persistent diarrhea

- Lung problems (interstitial fibrosis). Oxaliplatin injection can cause lung problems that may lead to death. Tell your doctor right away if you get a dry cough and have trouble breathing (shortness of breath) before your next treatment. These may be signs of a serious lung disease.
  - Liver problems (hepatotoxicity). Your doctor will do blood tests to check your liver.
  - Heart problems. Oxaliplatin injection can cause heart problems that have led to death. Your doctor may do blood and heart tests during treatment with oxaliplatin injection if you have certain heart problem. If you faint (lose consciousness) or have an irregular heartbeat or chest pain during treatment with oxaliplatin injection, tell your doctor right away as this may be a sign of a serious heart condition.
  - Muscle problems. Oxaliplatin injection can cause muscle damage (rhabdomyolysis) which can lead to death. Tell your doctor right away if you have muscle pain and swelling, along with weakness, fever, or red- brown urine.
  - Harm to an unborn baby. See “What should I tell my doctor before receiving oxaliplatin injection?”

The most common side effects of oxaliplatin injection include:

- Numbness, pain, tingling, and/or burning along the nerves
- Low white blood cells (neutropenia)
- Low platelet count (important for clotting and to control bleeding)
- Low red blood cells (blood cells that carry oxygen to the tissues)
- Nausea
- Changes in liver function tests
- Diarrhea
- Vomiting
- Tiredness
- Mouth sores

Tell your doctor if you have any side effect that bothers your or that does not go away. These are not all the possible side effects of oxaliplatin injection. For more information, ask your doctor or pharmacist.

Call your doctor for medical advice about side effects. You may report side effects to FDA at 1-800-FDA-1088.

How can I reduce the side effects caused by cold temperatures?

- Cover yourself with a blanket while you are getting your oxaliplatin injection infusion.
- Do not breathe deeply when exposed to cold air.
- Wear warm clothing in cold weather at all times. Cover your mouth and nose with a scarf or a pull-down cap (ski cap) to warm the air that goes to your lungs.
- Wear gloves when taking things from the freezer or refrigerator.
- Drink fluids warm or at room temperature.
- Always drink through a straw.
- Do not use ice chips if you have nausea or mouth sores. Ask your doctor about what you can use.
- Be aware that most metals are cold to touch, especially in the winter. These include your car door and mailbox. Wear gloves to touch cold objects.
- Do not run the air-conditioning at high levels in the house or in the car in hot weather.
- If your body gets cold, warm-up the affected part. If your hands get cold, wash them with warm water.
- Always let your doctor know before your next treatment how well you did since your last visit.

Your doctor may have other useful tips for helping you with side effects.

General information about the safe and effective use of oxaliplatin injection

Medicines are sometimes prescribed for purposes other than those listed in the Patient Information leaflet.

This Patient Information leaflet summarizes the most important information about oxaliplatin injection. If you would like more information, talk with your doctor. You can ask your doctor or pharmacist for information about oxaliplatin injection that is written for health professionals.

What are the ingredients in oxaliplatin injection?

Active ingredient: oxaliplatin

Inactive ingredients: water for injection

Distributed by:
Sun Pharmaceutical Industries, Inc.
Cranbury, NJ 08512
Manufactured by:
Sun Pharmaceutical Industries Ltd.
Halol-Baroda Highway,
Halol-389 350, Gujarat, India.
Under license from Sanofi-Aventis U.S. LLC,
Sanofi-Aventis, and Debiopharm S.A.
of U.S. Pat Nos. 5,420,319; 5,959,133; and 5,716,988
ISS. 10/2015
PJPI0332B

PACKAGE LABEL.PRINCIPAL DISPLAY PANEL - LABEL - 50MG

NDC 47335-046-40
Oxaliplatin Injection, USP
50 mg/10 mL (5 mg/mL)
Cytotoxic Agent
FOR INTRAVENOUS USE ONLY
Single Use Vial
Sterile - Preservative Free
See package insert for further required dilution
DO NOT MIX OR ADD TO SODIUM CHLORIDE/CHLORIDE-CONTAINING SOLUTIONS
Rx only
SUN PHARMA

PACKAGE LABEL.PRINCIPAL DISPLAY PANEL - CARTON - 50MG

NDC 47335-046-40
Oxaliplatin Injection, USP
50 mg/10 mL (5 mg/mL)
Cytotoxic Agent
FOR INTRAVENOUS USE ONLY
Single Use Vial Only
Sterile - Preservative Free
See package insert for further required dilution
DO NOT MIX OR ADD TO SODIUM CHLORIDE/CHLORIDE-CONTAINING SOLUTIONS
Rx only
10 mL Single-Use Vial
SUN PHARMA

PACKAGE LABEL.PRINCIPAL DISPLAY PANEL - LABEL - 100MG

NDC 47335-047-40
Oxaliplatin Injection, USP
100 mg/20 mL (5 mg/mL)
Cytotoxic Agent
FOR INTRAVENOUS USE ONLY
Single Use Vial
Sterile - Preservative Free
See package insert for further required dilution
DO NOT MIX OR ADD TO SODIUM CHLORIDE/CHLORIDE-CONTAINING SOLUTIONS
Rx only
SUN PHARMA

PACKAGE LABEL.PRINCIPAL DISPLAY PANEL - CARTON - 100MG

NDC 47335-047-40
Oxaliplatin Injection, USP
100 mg/20 mL (5 mg/mL)
Cytotoxic Agent
FOR INTRAVENOUS USE ONLY
SIngle Use Vial Only
Sterile - Preservative Free
See package insert for further required dilution
DO NOT MIX OR ADD TO SODIUM CHLORIDE/CHLORIDE-CONTAINING SOLUTIONS
Rx only
20 mL Single-Use Vial
SUN PHARMA